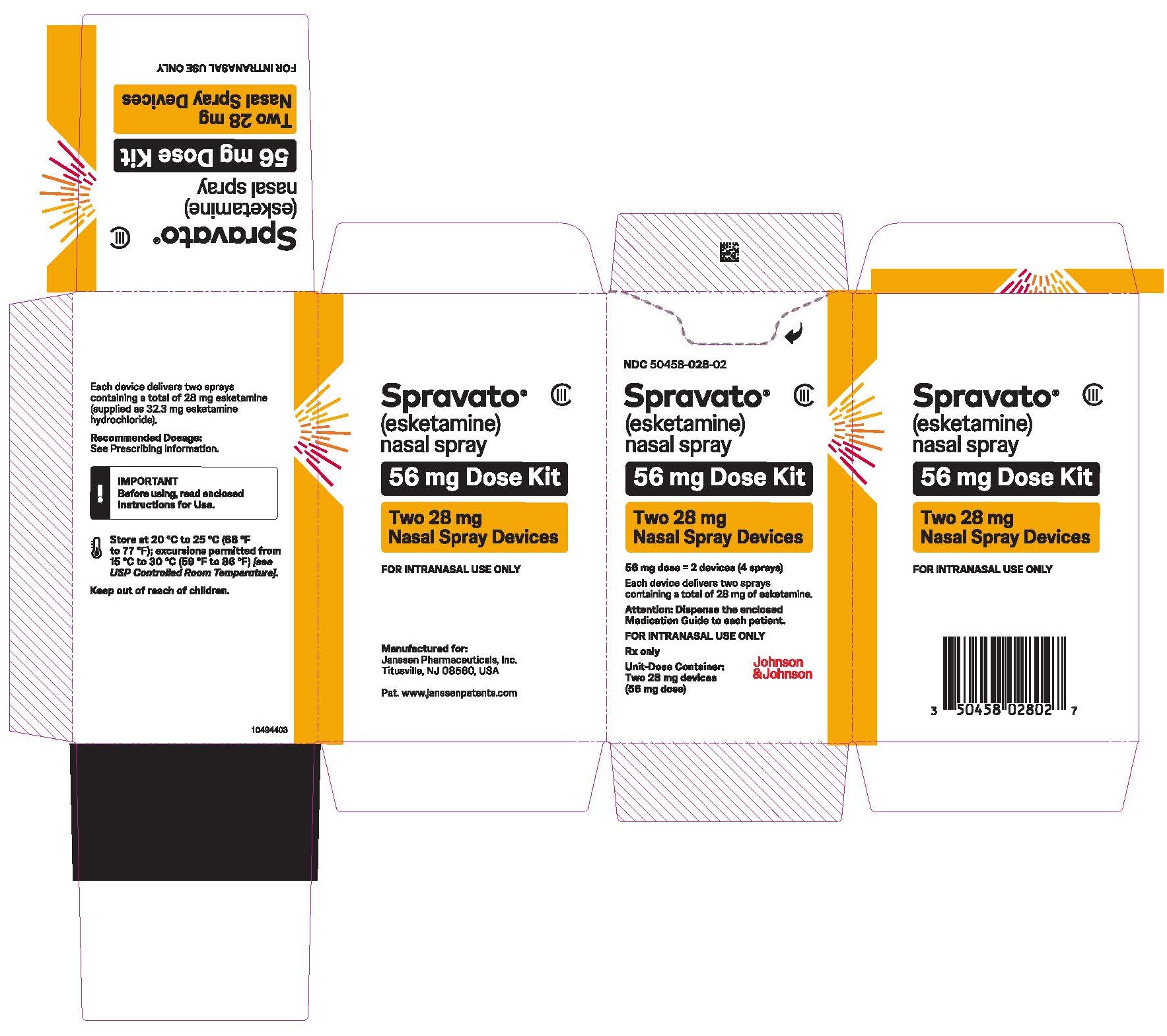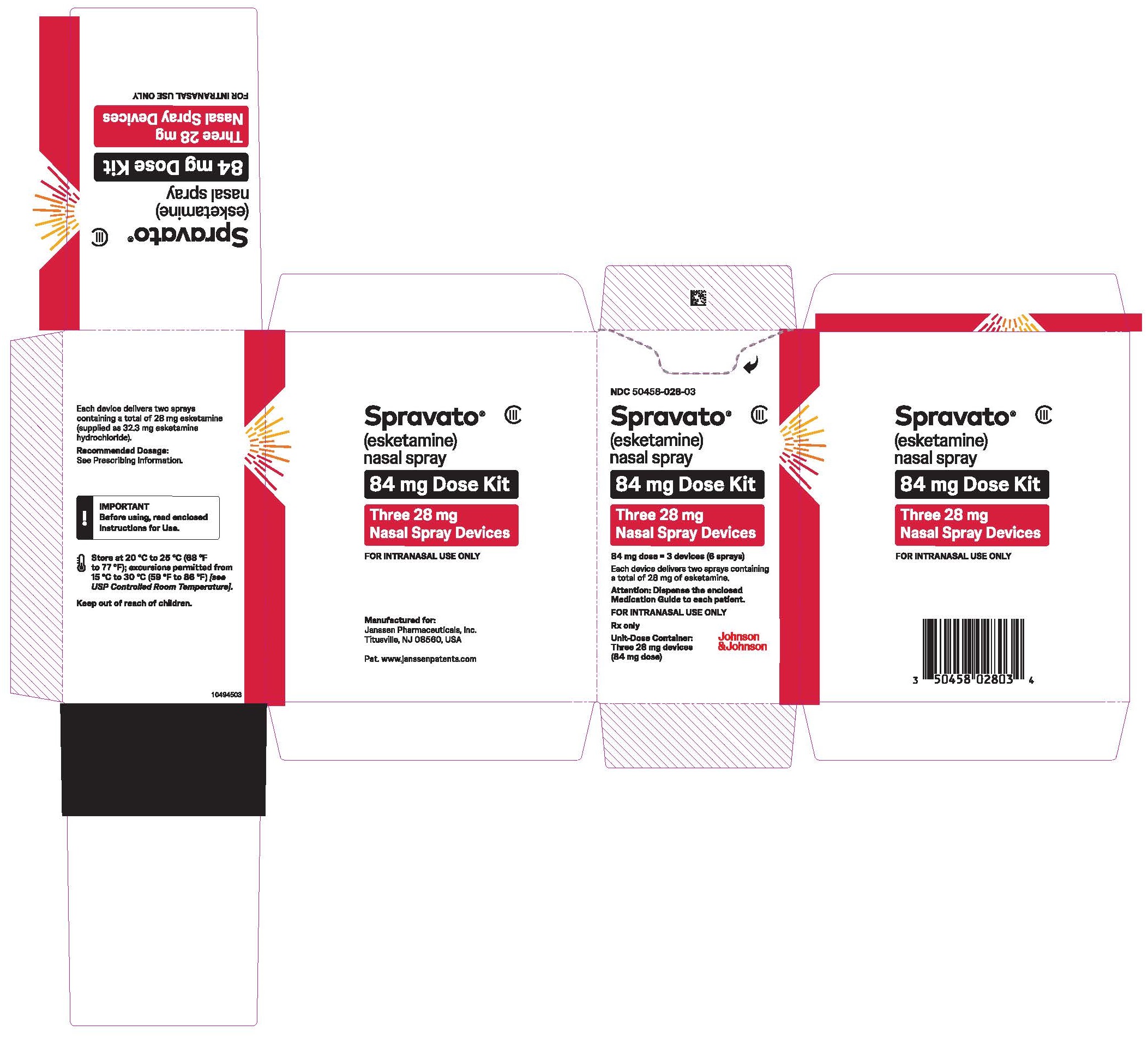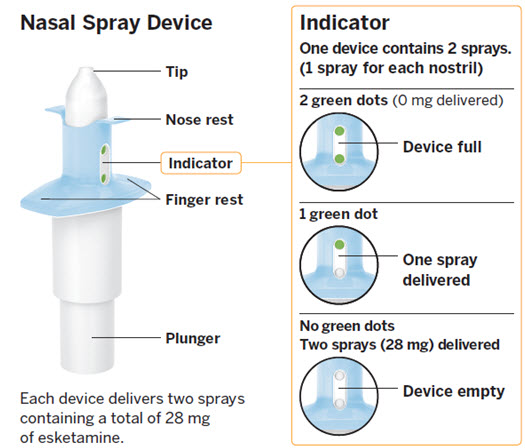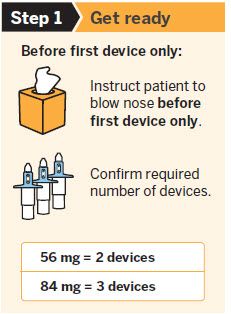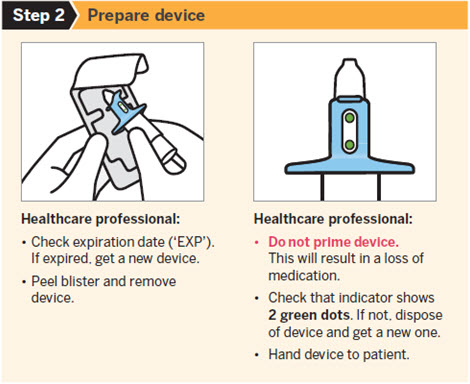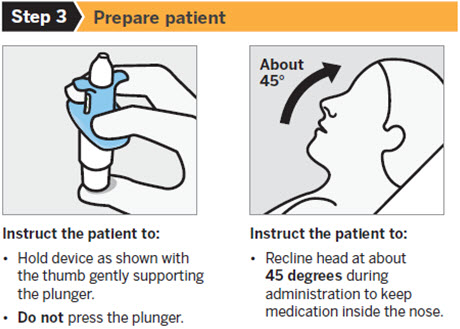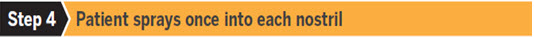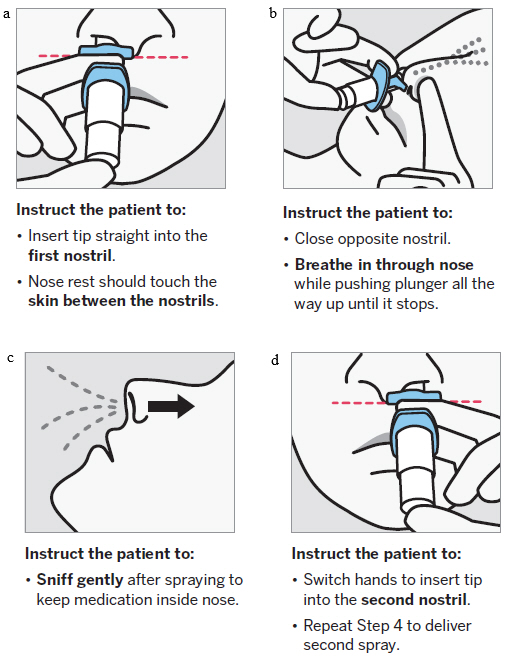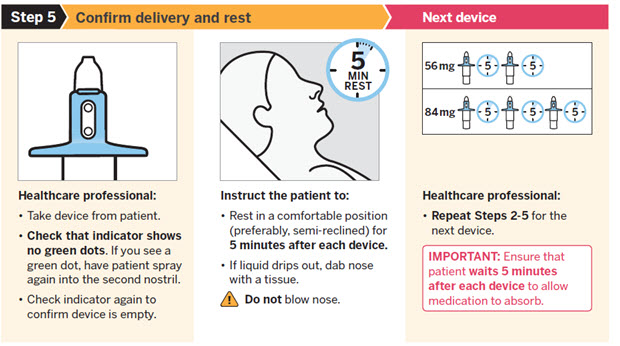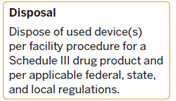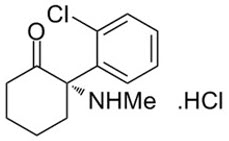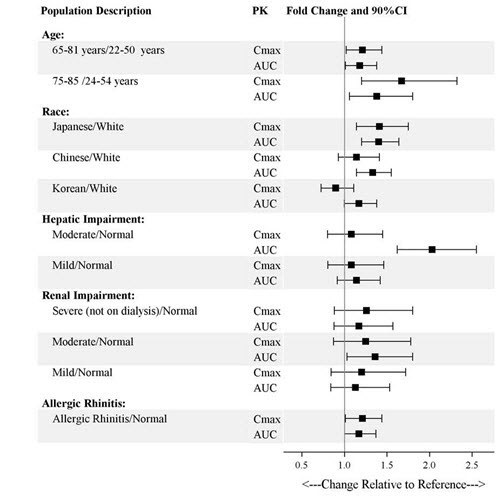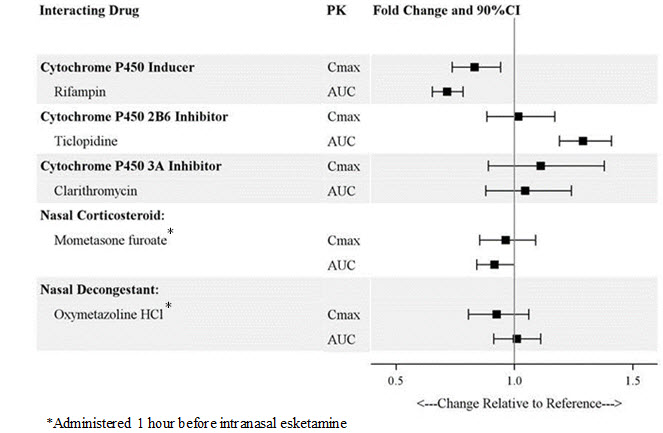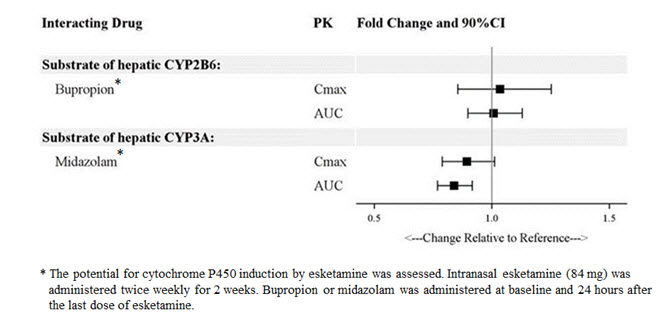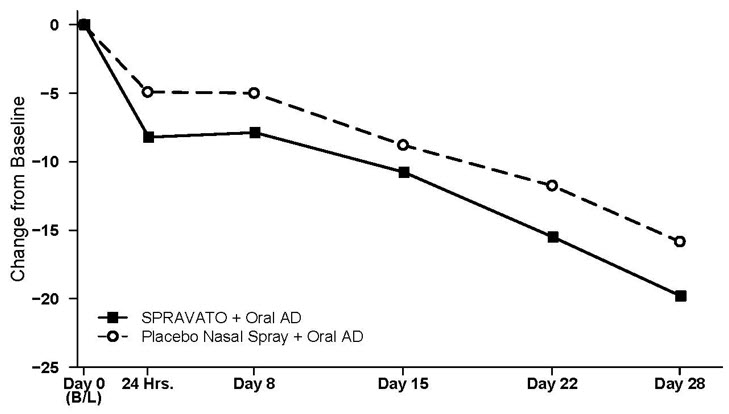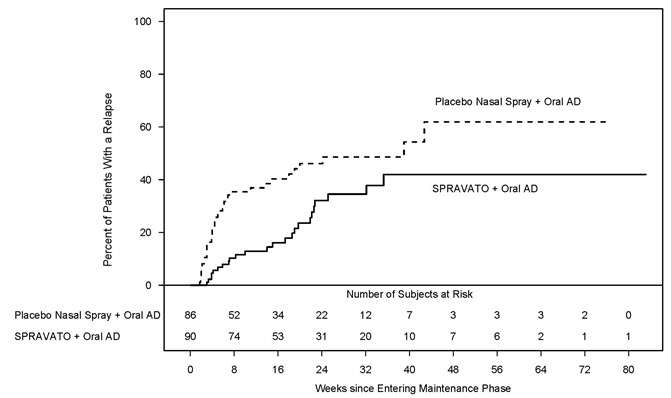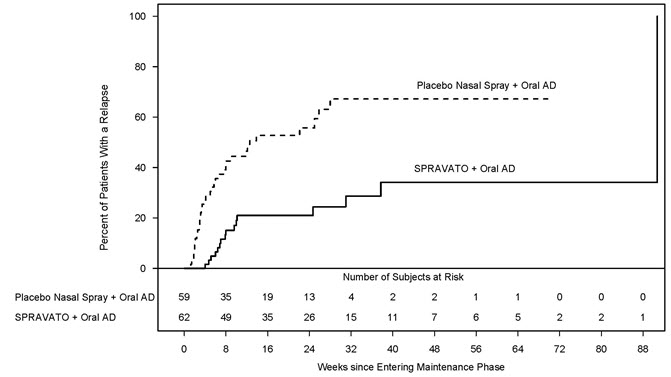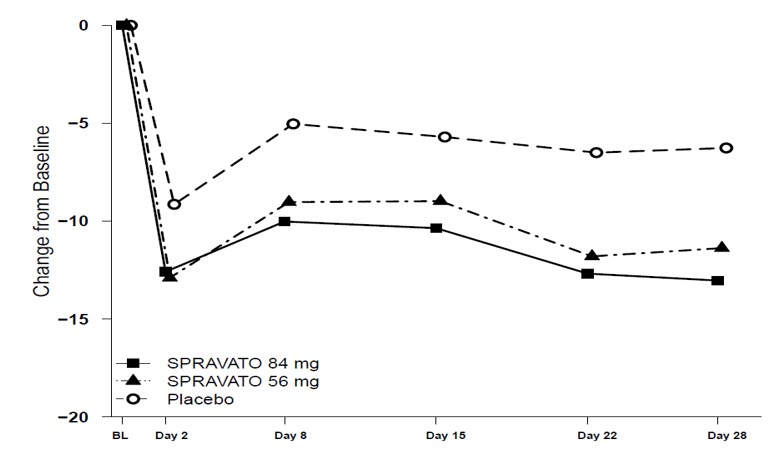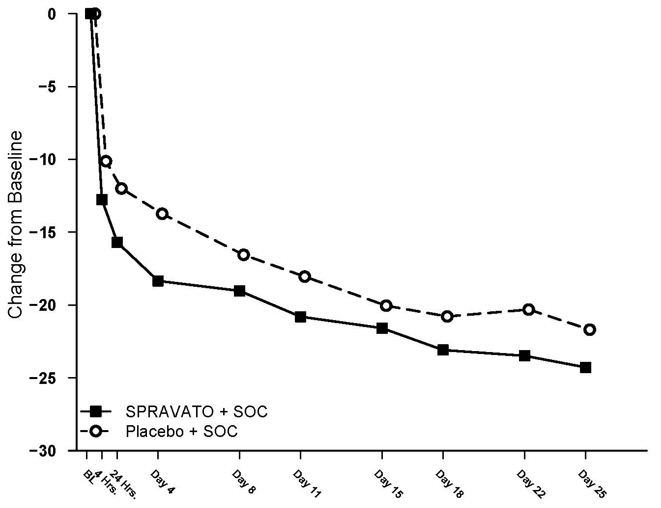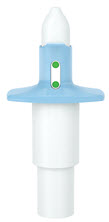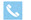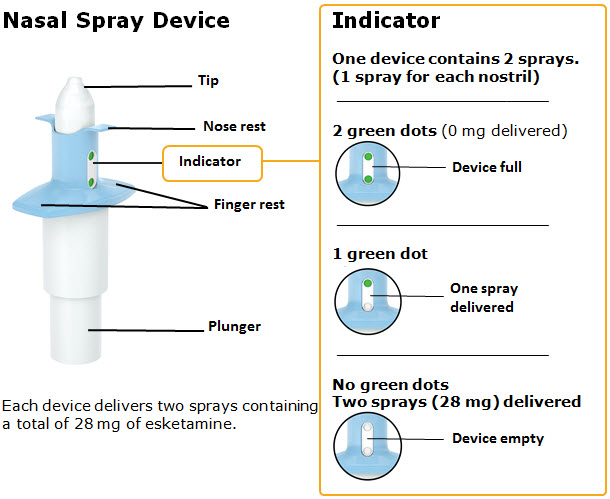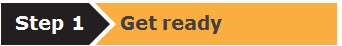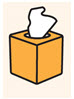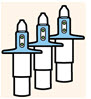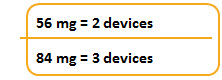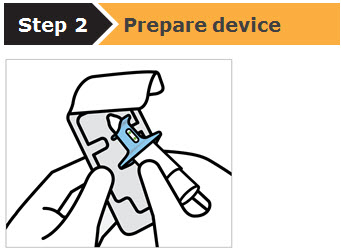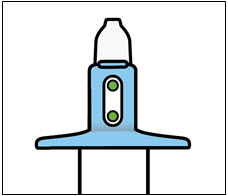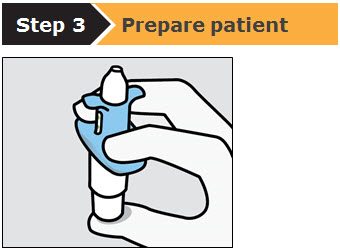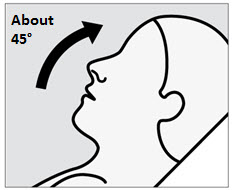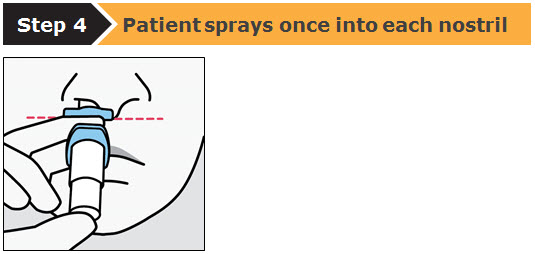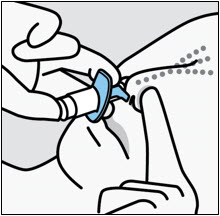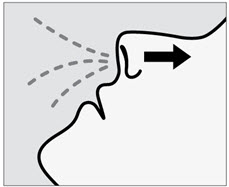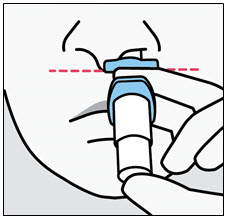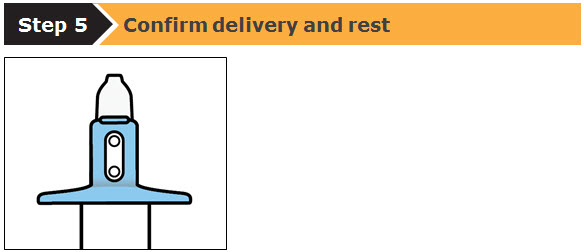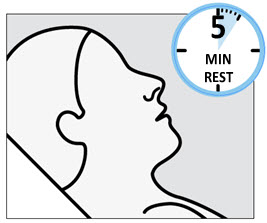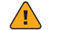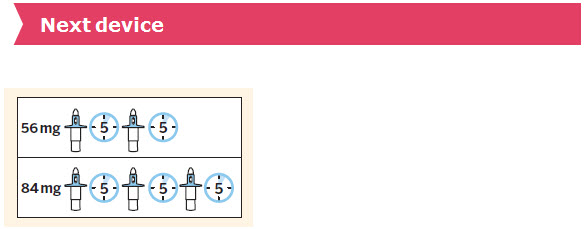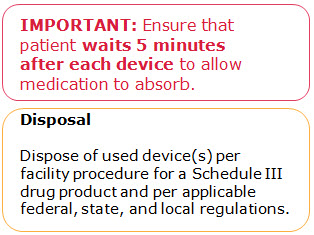 DRUG LABEL: Spravato
NDC: 50458-028 | Form: SOLUTION
Manufacturer: Janssen Pharmaceuticals Inc.
Category: prescription | Type: HUMAN PRESCRIPTION DRUG LABEL
Date: 20250826
DEA Schedule: CIII

ACTIVE INGREDIENTS: ESKETAMINE HYDROCHLORIDE 28 mg/0.2 mL
INACTIVE INGREDIENTS: CITRIC ACID MONOHYDRATE; EDETATE DISODIUM; SODIUM HYDROXIDE

HIGHLIGHTS OF PRESCRIBING INFORMATION

These highlights do not include all the information needed to use SPRAVATO safely and effectively. See full prescribing information for SPRAVATO.
SPRAVATO®(esketamine) nasal spray, CIII
Initial U.S. Approval: 1970 (ketamine)

WARNING: SEDATION; DISSOCIATION; RESPIRATORY DEPRESSION; ABUSE AND MISUSE; and SUICIDAL THOUGHTS AND BEHAVIORS

See full prescribing information for complete boxed warning.

- Risk for sedation, dissociation, and respiratory depression after administration. Monitor patients for at least two hours after administration. (5.1, 5.2, 5.3)
- Potential for abuse and misuse. Consider the risks and benefits of prescribing SPRAVATO prior to using in patients at higher risk of abuse. Monitor patients for signs and symptoms of abuse and misuse. (5.4)
- SPRAVATO is only available through a restricted program called the SPRAVATO REMS. (5.5)
- Increased risk of suicidal thoughts and behaviors in pediatric and young adult patients taking antidepressants. Closely monitor all antidepressant-treated patients for clinical worsening and emergence of suicidal thoughts and behaviors. SPRAVATO is not approved for use in pediatric patients. (5.6)

RECENT MAJOR CHANGES

Indications and Usage (1) | 01/2025
Dosage and Administration (2.2) | 01/2025
Warnings and Precautions (5.8) | 11/2024

1 INDICATIONS AND USAGE

SPRAVATO is a non-competitive N-methyl D-aspartate (NMDA) receptor antagonist indicated for the treatment of:

- Treatment-resistant depression (TRD) in adults, as monotherapy or in conjunction with an oral antidepressant. (1)
- Depressive symptoms in adults with major depressive disorder (MDD) with acute suicidal ideation or behavior in conjunction with an oral antidepressant. (1)

Limitations of Use:

- The effectiveness of SPRAVATO in preventing suicide or in reducing suicidal ideation or behavior has not been demonstrated. Use of SPRAVATO does not preclude the need for hospitalization if clinically warranted, even if patients experience improvement after an initial dose of SPRAVATO. (1)
- SPRAVATO is not approved as an anesthetic agent. The safety and effectiveness of SPRAVATO as an anesthetic agent have not been established. (1)

2 DOSAGE AND ADMINISTRATION

- Administer SPRAVATO intranasally under the supervision of a healthcare provider. (2.1)
- Assess blood pressure prior to and after administration. (2.1)
- TRD:Evidence of therapeutic benefit should be evaluated at the end of the 4-week induction phase to determine need for continued treatment. (2.2)
- Depressive symptoms in MDD with acute suicidal ideation or behavior: Evidence of therapeutic benefit should be evaluated after 4 weeks to determine need for continued treatment. Treatment beyond 4 weeks has not been systematically evaluated. (2.3)
- See Full Prescribing Information for recommended dosage. (2.2, 2.3)
- See Full Prescribing Information for important administration instructions. (2.4)

3 DOSAGE FORMS AND STRENGTHS

Nasal Spray: 28 mg of esketamine per device. Each nasal spray device delivers two sprays containing a total of 28 mg of esketamine. (3)

4 CONTRAINDICATIONS

- Aneurysmal vascular disease (including thoracic and abdominal aorta, intracranial and peripheral arterial vessels) or arteriovenous malformation. (4)
- Intracerebral hemorrhage. (4)
- Hypersensitivity to esketamine, ketamine, or any of the excipients. (4)

5 WARNINGS AND PRECAUTIONS

- Increases in Blood Pressure:Patients with cardiovascular and cerebrovascular conditions and risk factors may be at an increased risk of associated adverse effects. (5.7)
- Cognitive Impairment:SPRAVATO may impair attention, judgment, thinking, reaction speed and motor skills. (5.8)
- Impaired Ability to Drive and Operate Machinery:Do not drive or operate machinery until the next day after a restful sleep. (5.9)
- Embryo-fetal Toxicity:May cause fetal harm. Consider pregnancy planning and prevention in females of reproductive potential. (5.11, 8.1, 8.3)

6 ADVERSE REACTIONS

The most commonly observed adverse reactions (incidence ≥5% and at least twice that of placebo):

- TRD: dissociation, dizziness, nausea, sedation, vertigo, hypoesthesia, anxiety, lethargy, blood pressure increased, vomiting, feeling drunk, and headache. (6)
- Treatment of depressive symptoms in adults with MDD with acute suicidal ideation or behavior: dissociation, dizziness, sedation, blood pressure increased, hypoesthesia, vomiting, euphoric mood, and vertigo. (6)

To report SUSPECTED ADVERSE REACTIONS, contact Janssen Pharmaceuticals, Inc. at 1-800-JANSSEN (1-800-526-7736) or FDA at 1-800-FDA-1088 orwww.fda.gov/medwatch.

8 USE IN SPECIFIC POPULATIONS

- Lactation: Breastfeeding not recommended. (8.2)

FULL PRESCRIBING INFORMATION

WARNING: SEDATION; DISSOCIATION; RESPIRATORY DEPRESSION; ABUSE AND MISUSE; and SUICIDAL THOUGHTS AND BEHAVIORS

Sedation

- Patients are at risk for sedation after administration of SPRAVATO [see Warnings and Precautions (5.1)].

Dissociation

- Patients are at risk for dissociative or perceptual changes after administration of SPRAVATO [see Warnings and Precautions (5.2)].

Respiratory Depression

- Respiratory depression has been observed in postmarketing experience [see Warnings and Precautions (5.3)] .

Because of the risks of sedation, dissociation, and respiratory depression, patients must be monitored for at least 2 hours at each treatment session, followed by an assessment to determine when the patient is considered clinically stable and ready to leave the healthcare setting [see Warnings and Precautions (5.1, 5.2, 5.3)] .

Abuse and Misuse

- SPRAVATO has the potential to be abused and misused. Consider the risks and benefits of prescribing SPRAVATO prior to use in patients at higher risk of abuse. Monitor patients for signs and symptoms of abuse and misuse [see Warnings and Precautions (5.4)] .

Because of the risks of serious adverse outcomes resulting from sedation, dissociation, respiratory depression, abuse and misuse, SPRAVATO is only available through a restricted program under a Risk Evaluation and Mitigation Strategy (REMS) called the SPRAVATO REMS [see Warnings and Precautions (5.5)] .

Suicidal Thoughts and Behaviors

Antidepressants increased the risk of suicidal thoughts and behavior in pediatric and young adult patients in short-term studies. Closely monitor all antidepressant-treated patients for clinical worsening, and for emergence of suicidal thoughts and behaviors. SPRAVATO is not approved for use in pediatric patients [see Warnings and Precautions (5.6)] .

1 INDICATIONS AND USAGE

SPRAVATO is indicated for the treatment of:

- Treatment-resistant depression (TRD) in adults as monotherapy or in conjunction with an oral antidepressant
- Depressive symptoms in adults with major depressive disorder (MDD) with acute suicidal ideation or behavior in conjunction with an oral antidepressant

Limitations of Use

- The effectiveness of SPRAVATO in preventing suicide or in reducing suicidal ideation or behavior has not been demonstrated [see Clinical Studies (14.2)] . Use of SPRAVATO does not preclude the need for hospitalization if clinically warranted, even if patients experience improvement after an initial dose of SPRAVATO.
- SPRAVATO is not approved as an anesthetic agent. The safety and effectiveness of SPRAVATO as an anesthetic agent have not been established.

2 DOSAGE AND ADMINISTRATION

2.1 Important Considerations Prior to Initiating and During Therapy

SPRAVATO must be administered under the direct supervision of a healthcare provider. A treatment session consists of nasal administration of SPRAVATO and post-administration observation under supervision.

Respiratory Status Assessment During Treatment

- Monitor patients for changes in respiratory status for at least 2 hours (including pulse oximetry) at each treatment session [see Warnings and Precautions (5.3)] .

Blood Pressure Assessment Before and After Treatment

- Assess blood pressure prior to dosing with SPRAVATO [see Warnings and Precautions (5.7)] .
- If baseline blood pressure is elevated (e.g., >140 mmHg systolic, >90 mmHg diastolic), consider the risks of short term increases in blood pressure and benefit of SPRAVATO treatment [see Warnings and Precautions (5.7)]. Do not administer SPRAVATO if an increase in blood pressure or intracranial pressure poses a serious risk [see Contraindications (4)] .
- After dosing with SPRAVATO, reassess blood pressure at approximately 40 minutes (which corresponds with the Cmax) and subsequently as clinically warranted.
- If blood pressure is decreasing and the patient appears clinically stable for at least two hours, the patient may be discharged at the end of the post-dose monitoring period; if not, continue to monitor [see Warnings and Precautions (5.7)].

Food and Liquid Intake Recommendations Prior to Administration

Because some patients may experience nausea and vomiting after administration of SPRAVATO [see Adverse Reactions (6.1)], advise patients to avoid food for at least 2 hours before administration and to avoid drinking liquids at least 30 minutes prior to administration.

Nasal Corticosteroid or Nasal Decongestant

Patients who require a nasal corticosteroid or nasal decongestant on a dosing day should administer these medications at least 1 hour before SPRAVATO [see Clinical Pharmacology (12.3)].

2.2 Treatment-Resistant Depression

The recommended dosage of SPRAVATO for the treatment of TRD in adults as monotherapy or in conjunction with an oral antidepressant is shown in Table 1. Dosage adjustments should be made based on efficacy and tolerability. Evidence of therapeutic benefit should be evaluated at the end of the induction phase to determine need for continued treatment.

Table 1: Recommended Dosage for SPRAVATO for TRD
 |  | Adults
Induction Phase | Weeks 1 to 4:
 | Administer twice per week | 56 mg or 84 mg
Maintenance Phase | Weeks 5 to 8:
 | Administer once weekly | 56 mg or 84 mg
 | Week 9 and after:
 | Administer every 2 weeks or once weekly [Dosing frequency should be individualized to the least frequent dosing to maintain remission/response.] | 56 mg or 84 mg

2.3 Depressive Symptoms in Patients with Major Depressive Disorder with Acute Suicidal Ideation or Behavior

Administer SPRAVATO in conjunction with an oral antidepressant (AD).

The recommended dosage of SPRAVATO for the treatment of depressive symptoms in adults with MDD with acute suicidal ideation or behavior is 84 mg twice per week for 4 weeks. Dosage may be reduced to 56 mg twice per week based on tolerability. After 4 weeks of treatment with SPRAVATO, evidence of therapeutic benefit should be evaluated to determine need for continued treatment. The use of SPRAVATO, in conjunction with an oral antidepressant, beyond 4 weeks has not been systematically evaluated in the treatment of depressive symptoms in patients with MDD with acute suicidal ideation or behavior.

2.4 Administration Instructions

SPRAVATO is for nasal use only. The nasal spray device delivers a total of 28 mg of esketamine. To prevent loss of medication, do not prime the device before use. Use 2 devices (for a 56 mg dose) or 3 devices (for an 84 mg dose), with a 5-minute rest between use of each device. Follow these administration instructions and read the Instructions for Usebefore administration:

2.5 Post-Administration Observation

During and after SPRAVATO administration at each treatment session, observe the patient for at least 2 hours until the patient is safe to leave [see Warnings and Precautions (5.1, 5.2, 5.3, 5.7)] . Before SPRAVATO administration, instruct patients not to engage in potentially hazardous activities, such as driving a motor vehicle or operating machinery, until the next day after a restful sleep [see Warnings and Precautions (5.9)] .

2.6 Missed Treatment Session(s)

If a patient misses treatment session(s), provided there is no worsening of their depressive symptoms, the patient should continue the current dosing schedule.

For patients who miss treatment session(s) during maintenance treatment and have worsening of depression symptoms, per clinical judgement, consider returning to the previous dosing schedule (e.g., if doses missed during weekly dosing, revert to twice weekly dosing).

3 DOSAGE FORMS AND STRENGTHS

Nasal Spray: 28 mg of esketamine per device. Each nasal spray device delivers two sprays containing a total of 28 mg esketamine.

4 CONTRAINDICATIONS

SPRAVATO is contraindicated in patients with:

- Aneurysmal vascular disease (including thoracic and abdominal aorta, intracranial, and peripheral arterial vessels) or arteriovenous malformation [see Warnings and Precautions (5.7)]
- History of intracerebral hemorrhage [see Warnings and Precautions (5.7)]
- Hypersensitivity to esketamine, ketamine, or any of the excipients.

5 WARNINGS AND PRECAUTIONS

5.1 Sedation

SPRAVATO may cause sedation or loss of consciousness. In some cases, patients may display diminished or less apparent breathing. In clinical trials, 48% to 61% of SPRAVATO-treated patients developed sedation based on the Modified Observer's Assessment of Alertness/Sedation scale (MOAA/S) [see Adverse Reactions (6.1)] , and 0.3% to 0.4% of SPRAVATO-treated patients experienced loss of consciousness (MOAA/S score of 0).

Because of the possibility of delayed or prolonged sedation, patients must be monitored by a healthcare provider for at least 2 hours at each treatment session, followed by an assessment to determine when the patient is considered clinically stable and ready to leave the healthcare setting [see Dosage and Administration (2.5)] .

Closely monitor for sedation with concomitant use of SPRAVATO with CNS depressants [see Drug Interactions (7.1)] .

SPRAVATO is available only through a restricted program under a REMS [see Warnings and Precautions (5.5)] .

5.2 Dissociation

The most common psychological effects of SPRAVATO were dissociative or perceptual changes (including distortion of time, space and illusions), derealization and depersonalization (61% to 84% of SPRAVATO-treated patients developed dissociative or perceptual changes based on the Clinician-Administered Dissociative States Scale) [see Adverse Reactions (6.1)] . Given its potential to induce dissociative effects, carefully assess patients with psychosis before administering SPRAVATO; treatment should be initiated only if the benefit outweighs the risk.

Because of the risks of dissociation, patients must be monitored by a healthcare provider for at least 2 hours at each treatment session, followed by an assessment to determine when the patient is considered clinically stable and ready to leave the healthcare setting [see Dosage and Administration (2.5)] .

SPRAVATO is available only through a restricted program under a REMS [see Warnings and Precautions (5.5)] .

5.3 Respiratory Depression

In post marketing experience, respiratory depression was observed with the use of SPRAVATO. In addition, there were rare reports of respiratory arrest [see Adverse Reactions (6.2)] .

Because of the risks of respiratory depression, patients must be monitored for changes in respiratory status by a healthcare provider for at least 2 hours (including pulse oximetry) at each treatment session, followed by an assessment to determine when the patient is considered clinically stable and ready to leave the healthcare setting [see Dosage and Administration (2.5)] .

SPRAVATO is available only through a restricted program under a REMS [see Warnings and Precautions (5.5)] .

5.4 Abuse and Misuse

SPRAVATO contains esketamine, a Schedule III controlled substance (CIII), and may be subject to abuse and diversion. Assess each patient's risk for abuse or misuse prior to prescribing SPRAVATO and monitor all patients receiving SPRAVATO for the development of these behaviors or conditions, including drug-seeking behavior, while on therapy. Contact local state professional licensing board or state-controlled substances authority for information on how to prevent and detect abuse or diversion of SPRAVATO. Individuals with a history of drug abuse or dependence are at greater risk; therefore, use careful consideration prior to treatment of individuals with a history of substance use disorder and monitor for signs of abuse or dependence [see Drug Abuse and Dependence (9)] .

SPRAVATO is available only through a restricted program under a REMS [see Warnings and Precautions (5.5)] .

5.5 SPRAVATO Risk Evaluation and Mitigation Strategy (REMS)

SPRAVATO is available only through a restricted program under a REMS called the SPRAVATO REMS because of the risks of serious adverse outcomes from sedation, dissociation, respiratory depression, abuse and misuse [see Boxed Warningand Warnings and Precautions (5.1, 5.2, 5.3, 5.4)].

Important requirements of the SPRAVATO REMS include the following:

- Healthcare settings must be certified in the program and ensure that SPRAVATO is:
  - – Only dispensed and administered in healthcare settings.
  - – Patients treated in outpatient settings (e.g. medical offices and clinics) must be enrolled in the program.
  - – Administered by patients under the direct observation of a healthcare provider and that patients are monitored by a healthcare provider for at least 2 hours after administration of SPRAVATO [see Dosage and Administration (2.5)].
- Pharmacies must be certified in the REMS and must only dispense SPRAVATO to healthcare settings that are certified in the program.

Further information, including a list of certified pharmacies is available at www.SPRAVATOrems.com or 1-855-382-6022.

5.6 Suicidal Thoughts and Behaviors in Adolescents and Young Adults

In pooled analyses of placebo-controlled trials of antidepressant drugs (SSRIs and other antidepressant classes) that included approximately 77,000 adult patients and 4,500 pediatric patients (SPRAVATO is not approved in pediatric patients), the incidence of suicidal thoughts and behaviors in patients age 24 years and younger was greater than in placebo-treated patients. There was considerable variation in risk of suicidal thoughts and behaviors among drugs, but there was an increased risk identified in young patients for most drugs studied. There were differences in absolute risk of suicidal thoughts and behaviors across the different indications, with the highest incidence in patients with major depressive disorder (MDD). The drug-placebo differences in the number of cases of suicidal thoughts and behaviors per 1000 patients treated are provided in Table 2.

Table 2: Risk Differences of the Number of Patients with Suicidal Thoughts or Behaviors in the Pooled Placebo-Controlled Trials of Antidepressants in Pediatric [SPRAVATO is not approved in pediatric patients.] and Adult Patients
Age Range (Years) | Drug-Placebo Difference in Number of Patients with Suicidal Thoughts or Behaviors per 1000 Patients Treated
 | Increases Compared to Placebo
<18 | 14 additional patients
18–24 | 5 additional patients
 | Decreases Compared to Placebo
25–64 | 1 fewer patient
≥65 | 6 fewer patients

It is unknown whether the risk of suicidal thoughts and behaviors in children, adolescents, and young adults extends to longer-term use, i.e., beyond four months. However, there is substantial evidence from placebo-controlled maintenance studies in adults with MDD that antidepressants delay the recurrence of depression and that depression itself is a risk factor for suicidal thoughts and behaviors.

Monitor all antidepressant-treated patients for clinical worsening and emergence of suicidal thoughts and behaviors, especially during the initial few months of drug therapy and at times of dosage changes. Counsel family members or caregivers of patients to monitor for changes in behavior and to alert the healthcare provider. Consider changing the therapeutic regimen, including possibly discontinuing SPRAVATO and/or the concomitant oral antidepressant, in patients whose depression is persistently worse, or who are experiencing emergent suicidal thoughts or behaviors.

5.7 Increase in Blood Pressure

SPRAVATO causes increases in systolic and/or diastolic blood pressure (BP) at all recommended doses. Increases in BP peak approximately 40 minutes after SPRAVATO administration and last approximately 4 hours [see Adverse Reactions (6.1)] .

Approximately 3% to 19% of SPRAVATO-treated patients and 1% to 4% of placebo-treated patients experienced an increase of greater than or equal to 40 mmHg in systolic BP and/or 25 mmHg in diastolic BP in the first 1.5 hours after administration at least once during the first 4 weeks of treatment. A substantial increase in blood pressure could occur after any dose administered even if smaller blood pressure effects were observed with previous administrations. SPRAVATO is contraindicated in patients for whom an increase in BP or intracranial pressure poses a serious risk (e.g., aneurysmal vascular disease, arteriovenous malformation, history of intracerebral hemorrhage) [see Contraindications (4)]. Before prescribing SPRAVATO, patients with other cardiovascular and cerebrovascular conditions should be carefully assessed to determine whether the potential benefits of SPRAVATO outweigh its risks.

Assess BP prior to administration of SPRAVATO. In patients whose BP is elevated prior to SPRAVATO administration (as a general guide: >140/90 mmHg) a decision to delay SPRAVATO therapy should take into account the balance of benefit and risk in individual patients.

BP should be monitored for at least 2 hours after SPRAVATO administration [see Dosage and Administration (2.1, 2.5)] . Measure blood pressure around 40 minutes post-dose and subsequently as clinically warranted until values decline. If BP remains high, promptly seek assistance from practitioners experienced in BP management. Refer patients experiencing symptoms of a hypertensive crisis (e.g., chest pain, shortness of breath) or hypertensive encephalopathy (e.g., sudden severe headache, visual disturbances, seizures, diminished consciousness or focal neurological deficits) immediately for emergency care.

Closely monitor blood pressure with concomitant use of SPRAVATO with psychostimulants or monoamine oxidase inhibitors (MAOIs) [see Drug Interactions (7.2, 7.3)] .

In patients with history of hypertensive encephalopathy, more intensive monitoring, including more frequent blood pressure and symptom assessment, is warranted because these patients are at increased risk for developing encephalopathy with even small increases in blood pressure.

5.8 Cognitive Impairment

Short-Term Cognitive Impairment

In a study in healthy volunteers, a single dose of SPRAVATO caused cognitive performance decline 40 minutes post-dose. Compared to placebo-treated subjects, SPRAVATO-treated subjects required a greater effort to complete cognitive tests at 40 minutes post-dose. Cognitive performance and mental effort were comparable between SPRAVATO and placebo at 2 hours post-dose. Sleepiness was comparable after 4 hours post-dose.

Long-Term Cognitive Impairment

Long-term cognitive and memory impairment have been reported with repeated ketamine misuse or abuse. In 1-year and 3-year, long-term, open-label clinical trials in adults, the effect of SPRAVATO on cognitive functioning remained stable over time as evaluated by the Cogstate computerized battery and Hopkins Verbal Learning Test-Revised.

5.9 Impaired Ability to Drive and Operate Machinery

Two placebo-controlled studies were conducted to assess the effects of SPRAVATO on the ability to drive [see Clinical Studies (14.3)] . The effects of SPRAVATO 84 mg were comparable to placebo at 6 hours and 18 hours post-dose. However, two SPRAVATO-treated subjects in one of the studies discontinued the driving test at 8 hours post-dose because of SPRAVATO-related adverse reactions.

Before SPRAVATO administration, instruct patients not to engage in potentially hazardous activities requiring complete mental alertness and motor coordination, such as driving a motor vehicle or operating machinery, until the next day following a restful sleep. Patients will need to arrange transportation home following treatment with SPRAVATO.

5.10 Ulcerative or Interstitial Cystitis

Cases of ulcerative or interstitial cystitis have been reported in individuals with long-term off-label use or misuse/abuse of ketamine. In clinical studies with SPRAVATO nasal spray, there was a higher rate of lower urinary tract symptoms (pollakiuria, dysuria, micturition urgency, nocturia, and cystitis) in SPRAVATO-treated patients than in placebo-treated patients [see Adverse Reactions (6)] . No cases of esketamine-related interstitial cystitis were observed in any of the studies, which included treatment for up to a year.

Monitor for urinary tract and bladder symptoms during the course of treatment with SPRAVATO, and refer to an appropriate healthcare provider as clinically warranted.

5.11 Embryo-fetal Toxicity

Based on published findings from pregnant animals treated with ketamine, the racemic mixture of arketamine and esketamine, SPRAVATO may cause fetal harm when administered to pregnant women. Advise pregnant women of the potential risk to an infant exposed to SPRAVATO in utero. Advise women of reproductive potential to consider pregnancy planning and prevention [see Use in Specific Populations (8.1, 8.3)].

6 ADVERSE REACTIONS

The following adverse reactions are discussed in more detail in other sections of the labeling:

- Sedation [see Warnings and Precautions (5.1)]
- Dissociation [see Warnings and Precautions (5.2)]
- Respiratory Depression [see Warnings and Precautions (5.3)]
- Increase in Blood Pressure [see Warnings and Precautions (5.7)]
- Cognitive Impairment [see Warnings and Precautions (5.8)]
- Impaired Ability to Drive and Operate Machinery [see Warnings and Precautions (5.9)]
- Ulcerative or Interstitial Cystitis [see Warnings and Precautions (5.10)]
- Embryo-fetal Toxicity [see Warnings and Precautions (5.11)]

6.1 Clinical Trials Experience

Because clinical trials are conducted under widely varying conditions, adverse reaction rates observed in the clinical trials of a drug cannot be directly compared to rates in the clinical trials of another drug and may not reflect the rates observed in clinical practice.

Treatment-Resistant Depression

In Conjunction with an Oral Antidepressant

SPRAVATO was evaluated for safety in 1709 adults diagnosed with treatment-resistant depression (TRD) [see Clinical Studies (14.1)] from five Phase 3 studies (3 short-term and 2 long-term studies) and one Phase 2 dose-ranging study. Of all SPRAVATO-treated patients in the completed Phase 3 studies, 479 (30%) received at least 6 months of treatment, and 178 (11%) received at least 12 months of treatment.

Adverse Reactions Leading to Discontinuation of Treatment

In short-term studies in adults <65 years old (Study 1 pooled with another 4-week study), the proportion of patients who discontinued treatment because of an adverse reaction was 4.6% in patients who received SPRAVATO plus oral AD compared to 1.4% for patients who received placebo nasal spray plus oral AD. For adults ≥65 years old, the proportions were 5.6% and 3.1%, respectively. In Study 2, a long-term maintenance study, the discontinuation rates because of an adverse reaction were similar for patients receiving SPRAVATO plus oral AD and placebo nasal spray plus oral AD in the maintenance phase, at 2.6% and 2.1%, respectively. Across all Phase 3 studies, adverse reactions leading to SPRAVATO discontinuation in more than 2 patients were (in order of frequency): anxiety (1.2%), depression (0.9%), blood pressure increased (0.6%), dizziness (0.6%), suicidal ideation (0.5%), dissociation (0.4%), nausea (0.4%), vomiting (0.4%), headache (0.3%), muscular weakness (0.3%), vertigo (0.2%), hypertension (0.2%), panic attack (0.2%) and sedation (0.2%).

Most Common Adverse Reactions

The most commonly observed adverse reactions in patients treated with SPRAVATO plus oral AD (incidence ≥5% and at least twice that of placebo nasal spray plus oral AD) were dissociation, dizziness, nausea, sedation, vertigo, hypoesthesia, anxiety, lethargy, blood pressure increased, vomiting, and feeling drunk.

Table 3 shows the incidence of adverse reactions that occurred in patients treated with SPRAVATO plus oral AD at any dose and greater than patients treated with placebo nasal spray plus oral AD.

Table 3: Adverse Reactions Occurring in ≥2% of Adult TRD Patients Treated with SPRAVATO + Oral AD at Any Dose and at a Greater Rate than Patients Treated with Placebo Nasal Spray + Oral AD
 | SPRAVATO + Oral AD (N=346) | Placebo + Oral AD (N=222)
Cardiac disorders
Tachycardia [The following terms were combined: Anxiety includes: agitation; anticipatory anxiety; anxiety; fear; feeling jittery; irritability; nervousness; panic attack; tension Blood pressure increased includes: blood pressure diastolic increased; blood pressure increased; blood pressure systolic increased; hypertension Dissociation includes: delusional perception; depersonalization/derealization disorder; derealization; diplopia; dissociation; dysesthesia; feeling cold; feeling hot; feeling of body temperature change; hallucination; hallucination, auditory; hallucination, visual; hyperacusis; illusion; ocular discomfort; oral dysesthesia; paresthesia; paresthesia oral; pharyngeal paresthesia; photophobia; time perception altered; tinnitus; vision blurred; visual impairment Dizziness includes: dizziness; dizziness exertional; dizziness postural; procedural dizziness Dysarthria includes: dysarthria; slow speech; speech disorder Dysgeusia includes: dysgeusia; hypogeusia Headache includes: headache; sinus headache Hypoesthesia includes: hypoesthesia; hypoesthesia oral, hypoesthesia teeth, pharyngeal hypoesthesia Lethargy includes: fatigue; lethargy Nasal discomfort includes: nasal crusting; nasal discomfort; nasal dryness; nasal pruritus Sedation includes: altered state of consciousness; hypersomnia; sedation; somnolence Tachycardia includes: extrasystoles; heart rate increased; tachycardia Vertigo includes: vertigo; vertigo positional] | 6 (2%) | 1 (0.5%)
Ear and labyrinth disorders
Vertigo | 78 (23%) | 6 (3%)
Gastrointestinal disorders
Nausea | 98 (28%) | 19 (9%)
Vomiting | 32 (9%) | 4 (2%)
Diarrhea | 23 (7%) | 13 (6%)
Dry mouth | 19 (5%) | 7 (3%)
Constipation | 11 (3%) | 3 (1%)
General disorders and administration site conditions
Feeling drunk | 19 (5%) | 1 (0.5%)
Feeling abnormal | 12 (3%) | 0 (0%)
Investigations
Blood pressure increased | 36 (10%) | 6 (3%)
Nervous system disorders
Dizziness | 101 (29%) | 17 (8%)
Sedation | 79 (23%) | 21 (9%)
Headache | 70 (20%) | 38 (17%)
Dysgeusia | 66 (19%) | 30 (14%)
Hypoesthesia | 63 (18%) | 5 (2%)
Lethargy | 37 (11%) | 12 (5%)
Dysarthria | 15 (4%) | 0 (0%)
Tremor | 12 (3%) | 2 (1%)
Mental impairment | 11 (3%) | 2 (1%)
Psychiatric disorders
Dissociation | 142 (41%) | 21 (9%)
Anxiety | 45 (13%) | 14 (6%)
Insomnia | 29 (8%) | 16 (7%)
Euphoric mood | 15 (4%) | 2 (1%)
Renal and urinary disorders
Pollakiuria | 11 (3%) | 1 (0.5%)
Respiratory, thoracic and mediastinal disorders
Nasal discomfort | 23 (7%) | 11 (5%)
Throat irritation | 23 (7%) | 9 (4%)
Oropharyngeal pain | 9 (3%) | 5 (2%)
Skin and subcutaneous tissue disorders
Hyperhidrosis | 14 (4%) | 5 (2%)

Monotherapy

SPRAVATO used as monotherapy was evaluated for safety in 463 adults diagnosed with treatment-resistant depression (TRD) [see Clinical Studies (14.1)] .

Adverse Reactions Leading to Discontinuation of Treatment

In the double-blind treatment phase of the short-term study in adults (Study 3), the proportion of patients who discontinued treatment because of an adverse reaction was 1% in patients who received SPRAVATO 56 mg and 4% in patients who received SPRAVATO 84 mg compared to 1% for patients who received placebo nasal spray. All of the adverse reactions leading to SPRAVATO discontinuation occurred in single subjects.

Most Common Adverse Reactions

The most common adverse reactions (≥5% and at least twice that of placebo nasal spray) were dissociation, nausea, dizziness, headache, anxiety, vomiting, feeling drunk, blood pressure increased, and sedation. Table 4 shows the incidence of adverse reactions that occurred in patients treated with SPRAVATO and greater than patients treated with placebo nasal spray.

Table 4: Adverse Reactions Occurring in ≥2% of Adult TRD Patients Treated with SPRAVATO and at a Greater Rate than Patients Treated with Placebo Nasal Spray
 | SPRAVATO 56mg + 84mg (N=226) | Placebo (N=250)
Ear and labyrinth disorders
Vertigo | 6 (3%) | 0 (0%)
Gastrointestinal disorders
Nausea | 56 (25%) | 21 (8%)
Vomiting | 15 (7%) | 1 (<1%)
General disorders and administration site conditions
Feeling drunk | 16 (7%) | 2 (<1%)
Investigations
Blood pressure increased [The following terms were combined: Anxiety: anxiety, agitation, fear, feeling jittery, irritability, panic attack Blood pressure increased: blood pressure increased, hypertension Dissociation: depersonalization/derealization disorder, derealization, diplopia, dissociation, feeling hot, paresthesia, paresthesia oral, pharyngeal paresthesia, photophobia, tinnitus, vision blurred Dizziness: dizziness, dizziness postural Hypoesthesia: hypoesthesia, hypoesthesia oral, pharyngeal hypoesthesia Lethargy: fatigue, lethargy Sedation: sedation, somnolence] | 11 (5%) | 4 (2%)
Nervous system disorders
Disturbance in attention | 5(2%) | 0 (0%)
Dizziness | 50 (22%) | 18 (7%)
Sedation | 13 (6%) | 4 (2%)
Headache | 43 (19%) | 22 (9%)
Dysgeusia | 10 (4%) | 9 (4%)
Hypoesthesia | 10 (4%) | 1 (<1%)
Lethargy | 16 (7%) | 12 (5%)
Psychiatric disorders
Dissociation | 63 (28%) | 11 (4%)
Anxiety | 22 (10%) | 8 (3%)
Insomnia | 11 (5%) | 9 (4%)
Respiratory, thoracic, and mediastinal disorders
Throat irritation | 8 (4%) | 2 (1%)

Depressive Symptoms in Patients with Major Depressive Disorder with Acute Suicidal Ideation or Behavior

SPRAVATO was evaluated for safety in 262 adults for the treatment of depressive symptoms in adults with major depressive disorder (MDD) with acute suicidal ideation or behavior [see Clinical Studies (14.2)] from two Phase 3 studies (Study 4 and Study 5) and one Phase 2 study. Of all SPRAVATO-treated patients in the completed Phase 3 studies, 184 (81%) received all eight doses over a 4-week treatment period.

Adverse Reactions Leading to Discontinuation of Treatment

In short-term studies in adults (pooled Study 4 and Study 5), the proportion of patients who discontinued treatment because of an adverse reaction was 6.2% for patients who received SPRAVATO plus oral AD compared to 3.6% for patients who received placebo nasal spray plus oral AD. Adverse reactions leading to SPRAVATO discontinuation in more than 1 patient were (in order of frequency): dissociation-related events (2.6%), blood pressure increased (0.9%), dizziness-related events (0.9%), nausea (0.9%), and sedation-related events (0.9%).

Most Common Adverse Reactions

The most commonly observed adverse reactions in patients treated with SPRAVATO plus oral AD (incidence ≥5% and at least twice that of placebo nasal spray plus oral AD) were dissociation, dizziness, sedation, blood pressure increased, hypoesthesia, vomiting, euphoric mood, and vertigo. Table 5 shows the incidence of adverse reactions that occurred in patients treated with SPRAVATO plus oral AD and greater than patients treated with placebo nasal spray plus oral AD.

Table 5: Adverse Reactions Occurring in ≥2% of Adult Patients with MDD and Acute Suicidal Ideation or Behavior Treated with SPRAVATO + Oral AD and at a Greater Rate than Patients Treated with Placebo Nasal Spray + Oral AD
 | SPRAVATO + Oral AD (N=227) | Placebo + Oral AD (N=225)
Cardiac disorders
Tachycardia [The following terms were combined: Anxiety includes: agitation; anxiety; anxiety disorder; fear; irritability; nervousness; panic attack; psychomotor hyperactivity; tension Blood pressure increased includes: blood pressure diastolic increased; blood pressure increased; blood pressure systolic increased; hypertension Dissociation includes: depersonalization/derealization disorder; derealization; diplopia; dissociation; dysesthesia; feeling cold; feeling hot; hallucination; hallucination, auditory; hallucination, visual; hallucinations, mixed; hyperacusis; paresthesia; paresthesia oral; pharyngeal paresthesia; photophobia; time perception altered; tinnitus; vision blurred Dizziness includes: dizziness; dizziness exertional; dizziness postural Dysgeusia includes: dysgeusia; hypogeusia Hyperhidrosis includes: cold sweat; hyperhidrosis Hypoesthesia includes: hypoesthesia; hypoesthesia oral; intranasal hypoesthesia; pharyngeal hypoesthesia Lethargy includes: fatigue; lethargy; psychomotor retardation Pollakiuria includes: micturition urgency; pollakiuria Sedation includes: sedation; somnolence; stupor Tachycardia includes: heart rate increased; sinus tachycardia; tachycardia] | 8 (4%) | 2 (1%)
Ear and labyrinth disorders
Vertigo | 14 (6%) | 1 (0.4%)
Gastrointestinal disorders
Nausea | 61 (27%) | 31 (14%)
Vomiting | 26 (11%) | 12 (5%)
Constipation | 22 (10%) | 14 (6%)
Dry mouth | 8 (4%) | 6 (3%)
Toothache | 5 (2%) | 2 (1%)
General disorders and administration site conditions
Feeling drunk | 8 (4%) | 1 (0.4%)
Feeling of relaxation | 5 (2%) | 3 (1%)
Investigations
Blood pressure increased | 34 (15%) | 14 (6%)
Musculoskeletal and connective tissue disorders
Myalgia | 5 (2%) | 1 (0.4%)
Nervous system disorders
Dizziness | 103 (45%) | 34 (15%)
Sedation | 66 (29%) | 27 (12%)
Dysgeusia | 46 (20%) | 29 (13%)
Hypoesthesia | 30 (13%) | 4 (2%)
Lethargy | 10 (4%) | 4 (2%)
Confusional state | 5 (2%) | 0 (0%)
Psychiatric disorders
Dissociation | 108 (48%) | 30 (13%)
Anxiety | 34 (15%) | 20 (9%)
Euphoric mood | 17 (7%) | 1 (0.4%)
Intentional self-injury | 7 (3%) | 3 (1%)
Dysphoria | 5 (2%) | 0 (0%)
Renal and urinary disorders
Pollakiuria | 5 (2%) | 2 (1%)
Respiratory, thoracic and mediastinal disorders
Oropharyngeal pain | 10 (4%) | 3 (1%)
Throat irritation | 9 (4%) | 5 (2%)
Skin and subcutaneous tissue disorders
Hyperhidrosis | 11 (5%) | 5 (2%)

Sedation

Sedation was evaluated by adverse event reports and the Modified Observer's Assessment of Alertness/Sedation (MOAA/S). In the MOAA/S, 5 means "responds readily to name spoken in normal tone" and 0 means "no response after painful trapezius squeeze." Any decrease in MOAA/S from pre-dose is considered to indicate the presence of sedation, and such a decrease occurred in a higher number of patients on SPRAVATO than placebo during the short-term TRD studies. Dose-related increases in the incidence of sedation (MOAA/S score <5) were observed in a fixed-dose TRD study [see Warnings and Precautions (5.1)]. Table 6 presents the incidence of sedation (MOAA/S score <5) in a fixed-dose study with adult patients <65 years of age with TRD and a flexible-dose study with patients ≥65 years of age with TRD.

Table 6: Incidence of Sedation (MOAA/S Score <5) in Double-Blind, Randomized, Placebo-Controlled Studies (Fixed-Dose Study with Adult Patients <65 Years of Age with TRD and Flexible-Dose Study with Patients ≥65 Years of Age with TRD)
 | Patients <65 years |  |  | Patients ≥65 years
 | Placebo + Oral AD | SPRAVATO + Oral AD |  | Placebo + Oral AD | SPRAVATO + Oral AD
 |  | 56 mg | 84 mg |  | 28 to 84 mg
Number of patients [Patients who were evaluated with MOAA/S] | N=112 | N=114 | N=114 | N=63 | N=72
Sedation (MOAA/S score <5) | 11% | 50% | 61% | 19% | 49%

In studies for the treatment of depressive symptoms in adults with MDD with acute suicidal ideation or behavior, there was a higher incidence of sedation (MOAA/S score <5) in patients treated with SPRAVATO plus oral AD compared to patients treated with placebo plus oral AD, similar to the TRD study results in Table 5.

Dissociation/Perceptual Changes

SPRAVATO can cause dissociative symptoms (including derealization and depersonalization) and perceptual changes (including distortion of time and space, and illusions). In clinical trials, dissociation was transient and occurred on the day of dosing. Dissociation was evaluated by adverse event reports and the Clinician-Administered Dissociative States Scale (CADSS). A CADSS total score of more than 4 indicates the presence of dissociative symptoms, and such an increase to a score of 4 or more occurred in a higher number of patients on SPRAVATO compared to placebo during the short-term TRD studies. Dose-related increases in the incidence of dissociative symptoms (CADSS total score >4 and change >0) were observed in a fixed-dose TRD study [see Warnings and Precautions (5.2)] . Table 7 presents the incidence of dissociation (CADSS total score >4 and change >0) in a fixed-dose study with adult patients <65 years of age with TRD and a flexible-dose study with patients ≥65 years of age with TRD.

Table 7: Incidence of Dissociation (CADSS Total Score >4 and Change >0) in Double-Blind, Randomized, Placebo-Controlled Studies (Fixed-Dose Study with Adult Patients <65 Years of Age with TRD and Flexible-Dose Study with Patients ≥65 Years of Age with TRD)
 | Patients <65 years |  |  | Patients ≥65 years
 | Placebo + Oral AD | SPRAVATO + Oral AD |  | Placebo + Oral AD | SPRAVATO + Oral AD
 | Placebo + Oral AD | 56 mg | 84 mg | Placebo + Oral AD | 28 to 84 mg
Number of patients [Number of patients who were evaluated with CADSS] | N=113 | N=113 | N=116 | N=65 | N=72
CADSS total score >4 and change >0 | 5% | 61% | 69% | 12% | 75%

In studies for the treatment of depressive symptoms in adults with MDD with acute suicidal ideation or behavior, patients treated with SPRAVATO plus oral AD also demonstrated a higher number (84%) with dissociation (CADSS total score >4 and change >0) compared to patients treated with placebo plus oral AD (16%).

Increase in Blood Pressure

The mean placebo-adjusted increases in systolic and diastolic blood pressure (SBP and DBP) over time were about 7 to 10 mmHg in SBP and 4 to 6 mmHg in DBP at 40 minutes post-dose and 2 to 5 mmHg in SBP and 1 to 3 mmHg in DBP at 1.5 hours post-dose in patients with TRD receiving SPRAVATO [see Warnings and Precautions (5.7)] . Table 8 presents increases in blood pressure in short-term trials with patients <65 years of age and ≥65 years of age with TRD.

Table 8: Increases in Blood Pressure in Double-blind, Randomized, Placebo-Controlled, Short-Term Trials of SPRAVATO Compared to Placebo Nasal Spray in the Treatment of TRD in Adult Patients
 | SPRAVATO + Oral AD |  |  |  | SPRAVATO Monotherapy
 | Patients <65 years |  | Patients ≥65 years |  | Adult patients including those ≥65 years
 | SPRAVATO + Oral AD N=346 | Placebo + Oral AD N=222 | SPRAVATO + Oral AD N=72 | Placebo + Oral AD N=65 | SPRAVATO N=226 | Placebo N=250
Systolic blood pressure
≥180 mmHg | 9 (3%) | --- | 2 (3%) | 1 (2%) | 2 (0.9%) | 0
≥40 mmHg increase | 29 (8%) | 1 (0.5%) | 12 (17%) | 1 (2%) | 18 (8%) | 5 (2%)
Diastolic blood pressure
≥110 mmHg | 13 (4%) | 1 (0.5%) | --- | --- | 3 (1%) | 0
≥25 mmHg increase | 46 (13%) | 6 (3%) | 10 (14%) | 2 (3%) | 25 (11%) | 6 (2%)

In studies for the treatment of depressive symptoms in adults with MDD with acute suicidal ideation or behavior, patients treated with SPRAVATO plus oral antidepressants demonstrated similar mean placebo-adjusted increases in SBP and DBP compared to patients with TRD, as well as similar rates of increases to SBP ≥180 mmHg or ≥40 mmHg increases in SBP, and similar rates of increases to DBP ≥110 mmHg or ≥25 mmHg increases in DBP, compared to the TRD study results in Table 8.

Nausea and Vomiting

SPRAVATO can cause nausea and vomiting. Most of these events occurred on the day of dosing and resolved the same day, with the median duration not exceeding 1 hour in most subjects across dosing sessions. Rates of reported nausea and vomiting decreased over time across dosing sessions from the first week of treatment in the short-term studies, as well as over time with long-term treatment. Table 9 presents the incidence and severity of nausea and vomiting in a short-term study with patients with TRD.

Table 9: Incidence and Severity of Nausea and Vomiting in a Double-blind, Randomized, Placebo-Controlled, Fixed-Dose Study in Adult Patients with TRD
 |  | Nausea |  | Vomiting
Treatment (+ Oral AD)
 | N | All | Severe | All | Severe
SPRAVATO 56 mg | 115 | 31 (27%) | 0 | 7 (6%) | 0
SPRAVATO 84 mg | 116 | 37 (32%) | 4 (3%) | 14 (12%) | 3 (3%)
Placebo Nasal Spray | 113 | 12 (11%) | 0 | 2 (2%) | 0

In studies for the treatment of depressive symptoms in adults with MDD with acute suicidal ideation or behavior, patients demonstrated similar incidence and severity of reported nausea and vomiting compared to the TRD study results described above.

Sense of Smell

Sense of smell was assessed over time; no difference was observed between patients treated with SPRAVATO plus oral AD and those treated with placebo nasal spray plus oral AD during the double-blind maintenance phase of Study 2 [see Clinical Studies (14.1)] .

6.2 Postmarketing Experience

The following adverse reactions have been identified during post-approval use of SPRAVATO. Because these reactions are reported voluntarily, it is not always possible to reliably estimate their frequency or establish a causal relationship to drug exposure.

Cardiac disorders:bradycardia

Respiratory, thoracic and mediastinal disorders:respiratory depression (including respiratory arrest)

Vascular disorders:hypotension

7 DRUG INTERACTIONS

7.1 Central Nervous System Depressants

Concomitant use with CNS depressants (e.g., benzodiazepines, opioids, alcohol) may increase sedation [see Warnings and Precautions (5.1)] . Closely monitor for sedation with concomitant use of SPRAVATO with CNS depressants.

7.2 Psychostimulants

Concomitant use with psychostimulants (e.g., amphetamines, methylphenidate, modafinil, armodafinil) may increase blood pressure [see Warnings and Precautions (5.7)] . Closely monitor blood pressure with concomitant use of SPRAVATO with psychostimulants.

7.3 Monoamine Oxidase Inhibitors (MAOIs)

Concomitant use with monoamine oxidase inhibitors (MAOIs) may increase blood pressure [see Warnings and Precautions (5.7)] . Closely monitor blood pressure with concomitant use of SPRAVATO with MAOIs.

8 USE IN SPECIFIC POPULATIONS

8.1 Pregnancy

Pregnancy Exposure Registry

There is a pregnancy exposure registry that monitors pregnancy outcomes in women exposed to antidepressants, including SPRAVATO, during pregnancy. Healthcare providers are encouraged to register patients by contacting the National Pregnancy Registry for Antidepressants at 1-844-405-6185 or online at https://womensmentalhealth.org/clinical-and-research-programs/pregnancyregistry/antidepressants/.

Risk Summary

SPRAVATO is not recommended during pregnancy. There are insufficient data on SPRAVATO use in pregnant women to draw conclusions about any drug-associated risk of major birth defects, miscarriage, or adverse maternal or fetal outcomes. Based on published findings from pregnant animals treated with ketamine, the racemic mixture of arketamine and esketamine, SPRAVATO may cause fetal harm when administered to pregnant women (see Data) . Advise pregnant women of the potential risk to an infant exposed to SPRAVATO in utero. There are risks to the mother associated with untreated depression in pregnancy (see Clinical Considerations). If a woman becomes pregnant while being treated with SPRAVATO, treatment with esketamine should be discontinued and the patient should be counseled about the potential risk to the fetus.

Published studies in pregnant primates demonstrate that the administration of drugs that block N-methyl- D-aspartate (NMDA) receptors during the period of peak brain development increases neuronal apoptosis in the developing brain of the offspring. There are no data on pregnancy exposures in primates corresponding to periods prior to the third trimester in humans [see Use in Specific Populations (8.2)] .

In an embryo-fetal reproduction study in rabbits, skeletal malformations were noted at maternally toxic doses when ketamine was intranasally administered with a No Observed Adverse Effect Level (NOAEL) at estimated esketamine exposures 0.3 times the exposures at the maximum recommended human dose (MRHD) of 84 mg/day. In addition, intranasal administration of esketamine to pregnant rats during pregnancy and lactation at exposures that were similar to those at the MRHD resulted in a delay in sensorimotor development in pups during the preweaning period and a decrease in motor activity in the post-weaning period.

The estimated background risk of major birth defects and miscarriage for the indicated population is unknown. All pregnancies have a background risk of birth defect, loss, or other adverse outcomes. In the U.S. general population, the estimated background risk of major birth defects and miscarriage in clinically recognized pregnancies is 2 to 4% and 15 to 20%, respectively.

Clinical Considerations

Disease-Associated Maternal and/or Embryo-Fetal Risk

A prospective, longitudinal study followed 201 pregnant women with a history of major depressive disorder who were euthymic and taking antidepressants at the beginning of pregnancy. The women who discontinued antidepressants during pregnancy were more likely to experience a relapse of major depression than women who continued antidepressants. Consider the risk of untreated depression when discontinuing or changing treatment with antidepressant medication during pregnancy and postpartum.

Data

Animal Data

Based on published data, when female monkeys were treated intravenously with racemic ketamine at anesthetic dose levels in the third trimester of pregnancy, neuronal cell death was observed in the brains of their fetuses. This period of brain development translates into the third trimester of human pregnancy. The clinical significance of these findings is not clear; however, studies in juvenile animals suggest neuroapoptosis correlates with long-term cognitive deficits.

Racemic ketamine was administered intranasally to pregnant rats during the period of organogenesis at doses of 15, 50, and 150 mg/kg/day. The No Observed Adverse Effect Level (NOAEL) for embryo-fetal toxicity in rats was the highest dose of 150 mg/kg/day. Estimating 50% of the exposure to be from esketamine, the NOAEL associated with esketamine plasma exposure (AUC) is 12-times the AUC exposure at the MRHD of 84 mg/day. In pregnant rabbits, racemic ketamine was administered intranasally from gestational day 6 to 18 at doses of 10, 30, and 100 mg/kg/day. The high dose was lowered from 100 to 50 mg/kg after 5 days of dosing due to excessive mortality in the pregnant rabbits. Skeletal malformations were observed at doses ≥ 30 mg/kg/day, which were maternally toxic. The NOAEL for skeletal malformations was associated with a plasma esketamine exposure (AUC) that was 0.3 times the AUC exposure at MRHD of 84 mg/day.

Administration of esketamine to pregnant rats during pregnancy and lactation at intranasal doses equivalent to 4.5, 15, and 45 mg/kg/day (based on a 200-gram rat) produced AUC exposures 0.07, 0.5, and 0.7 times the MRHD of 84 mg/day, respectively. Maternal toxicity was observed at doses ≥ 15 mg/kg/day. In addition, a dose-dependent delay in the age of attainment of Preyer response reflex was observed in pups at all doses during the preweaning period. This sensory/motor developmental measure was tested starting on postnatal day (PND) 9, and the effect normalized by PND 19 in treatment groups as compared with PND 14 for the majority of the control animals. There is no NOAEL for this delay in sensory/motor response observed in pups during the preweaning period. During the postweaning period, a decrease in motor activity was observed at doses ≥ 15 mg/kg which is 0.5-times the human exposure at the MRHD of 84 mg/day. The NOAEL for maternal toxicity and decreased motor activity during the postweaning period was 4.5 mg/kg/day which was associated with a plasma exposure (AUC) that was 0.07-times the AUC exposure at MRHD of 84 mg/day.

8.2 Lactation

Risk Summary

Esketamine is present in human milk. There are no data on the effects of SPRAVATO on the breastfed infant or on milk production. Published studies in juvenile animals report neurotoxicity (see Data). Because of the potential for neurotoxicity, advise patients that breast-feeding is not recommended during treatment with SPRAVATO.

Data

Published juvenile animal studies demonstrate that the administration of drugs that block NMDA receptors, such as ketamine, during the period of rapid brain growth or synaptogenesis, results in widespread neuronal and oligodendrocyte cell loss in the developing brain and alterations in synaptic morphology and neurogenesis. Based on comparisons across species, the window of vulnerability to these changes is believed to correlate with exposures in the third trimester of gestation through the first several months of life, but this window may extend out to approximately 3 years of age in humans.

8.3 Females and Males of Reproductive Potential

Contraception

Based on published animal reproduction studies, SPRAVATO may cause embryo-fetal harm when administered to a pregnant woman [see Warnings and Precautions (5.11)and Use in Specific Populations (8.1)]. However, it is not clear how these animal findings relate to females of reproductive potential treated with the recommended clinical dose. Consider pregnancy planning and prevention for females of reproductive potential during treatment with SPRAVATO.

8.4 Pediatric Use

The safety and effectiveness of SPRAVATO in pediatric patients have not been established.

8.5 Geriatric Use

Of the total number of patients in randomized, double-blind, placebo-controlled short-term clinical studies exposed to SPRAVATO, (N=2064), 238 (12%) were 65 years of age and older, and 29 (1%) were 75 years of age and older. No overall differences in the safety profile were observed between patients 65 years of age and older and patients younger than 65 years of age.

The mean esketamine Cmaxand AUC values were higher in elderly patients compared with younger adult patients [see Clinical Pharmacology (12.3)] .

The efficacy of SPRAVATO for the treatment of TRD in geriatric patients was evaluated in a 4-week, randomized, double-blind study comparing flexibly-dosed intranasal SPRAVATO plus a newly initiated oral antidepressant compared to intranasal placebo plus a newly initiated oral antidepressant in patients ≥ 65 years of age. SPRAVATO was initiated at 28 mg twice weekly and could be titrated to 56 mg or 84 mg administered twice weekly. At the end of four weeks, there was no statistically significant difference between groups on the primary efficacy endpoint of change from baseline to Week 4 on the Montgomery-Åsberg Depression Rating Scale (MADRS).

8.6 Hepatic Impairment

The mean esketamine AUC and t1/2values were higher in patients with moderate hepatic impairment compared to those with normal hepatic function [see Clinical Pharmacology (12.3)] . SPRAVATO-treated patients with moderate hepatic impairment may need to be monitored for adverse reactions for a longer period of time.

SPRAVATO has not been studied in patients with severe hepatic impairment (Child-Pugh class C). Use in this population is not recommended [see Clinical Pharmacology (12.3)].

9 DRUG ABUSE AND DEPENDENCE

9.1 Controlled Substance

SPRAVATO contains esketamine hydrochloride, the (S)-enantiomer of ketamine and a Schedule III controlled substance under the Controlled Substances Act.

9.2 Abuse

Individuals with a history of drug abuse or dependence may be at greater risk for abuse and misuse of SPRAVATO. Abuse is the intentional, non-therapeutic use of a drug, even once, for its psychological or physiological effects. Misuse is the intentional use, for therapeutic purposes, of a drug by an individual in a way other than prescribed by a healthcare provider or for whom it was not prescribed. Careful consideration is advised prior to use of individuals with a history of substance use disorder, including alcohol.

SPRAVATO may produce a variety of symptoms including anxiety, dysphoria, disorientation, insomnia, flashback, hallucinations, and feelings of floating, detachment and to be "spaced out". Monitoring for signs of abuse and misuse is recommended.

Abuse Potential Study

A cross-over, double-blind abuse potential study of SPRAVATO and ketamine was conducted in recreational polydrug users (n=34) who had experience with perception-altering drugs, including ketamine. Ketamine, the racemic mixture of arketamine and esketamine, is a Schedule III controlled substance and has known abuse potential. In this study, the mean "Drug Liking at the Moment" and "Take Drug Again" scores for single doses of intranasal SPRAVATO (84 mg and 112 mg – the maximum recommended dose and 1.3 times the maximum recommended dose, respectively) were similar to these scores in the intravenous ketamine (0.5 mg/kg infused over 40 minutes) control group. However, these scores were greater in the SPRAVATO and ketamine groups compared to the placebo group. The 112 mg dose of intranasal SPRAVATO was associated with significantly higher scores for "Hallucinating," "Floating," "Detached," and "Spaced Out" than the 84 mg dose of intranasal SPRAVATO and the intravenous ketamine dose.

9.3 Dependence

Physical dependence has been reported with prolonged use of ketamine. Physical dependence is a state that develops as a result of physiological adaptation in response to repeated drug use, manifested by withdrawal signs and symptoms after abrupt discontinuation or significant dosage reduction of a drug. There were no withdrawal symptoms captured up to 4 weeks after cessation of esketamine treatment. Withdrawal symptoms have been reported after the discontinuation of frequently used (more than weekly) large doses of ketamine for long periods of time. Such withdrawal symptoms are likely to occur if esketamine were similarly abused. Reported symptoms of withdrawal associated with daily intake of large doses of ketamine include craving, fatigue, poor appetite, and anxiety. Therefore, monitor SPRAVATO-treated patients for symptoms and signs of physical dependence upon the discontinuation of the drug.

Tolerance has been reported with prolonged use of ketamine. Tolerance is a physiological state characterized by a reduced response to a drug after repeated administration (i.e., a higher dose of a drug is required to produce the same effect that was once obtained at a lower dose). Similar tolerance would be expected with prolonged use of esketamine.

10 OVERDOSAGE

Management of Overdosage

There is no specific antidote for esketamine overdose. In the case of overdose, the possibility of multiple drug involvement should be considered. Contact a Certified Poison Control Center for the most up to date information on the management of overdosage (1-800-222-1222 or www.poison.org).

11 DESCRIPTION

SPRAVATO®contains esketamine hydrochloride, a non-competitive N-methyl- D-aspartate (NMDA) receptor antagonist. Esketamine is the S-enantiomer of racemic ketamine. The chemical name is (S)-2-(o-chlorophenyl)-2-(methylamino)cyclohexanone hydrochloride. Its molecular formula is C13H16ClNO.HCl and its molecular weight is 274.2. The structural formula is:

Esketamine hydrochloride is a white or almost white crystalline powder that is freely soluble in water and in methanol, and soluble in ethanol.

SPRAVATO nasal spray is intended for nasal administration. Esketamine hydrochloride is contained as a solution in a stoppered glass vial within the nasal spray device. Each device delivers two sprays with a total of 32.3 mg of esketamine hydrochloride (equivalent to 28 mg of esketamine) in 0.2 mL of a clear, colorless aqueous solution with a pH of 4.5.

The inactive ingredients are citric acid monohydrate, edetate disodium, sodium hydroxide, and water for injection.

12 CLINICAL PHARMACOLOGY

12.1 Mechanism of Action

Esketamine, the S-enantiomer of racemic ketamine, is a non-selective, non-competitive antagonist of the N-methyl- D-aspartate (NMDA) receptor, an ionotropic glutamate receptor. The mechanism by which esketamine exerts its antidepressant effect is unknown. The major circulating metabolite of esketamine (noresketamine) demonstrated activity at the same receptor with less affinity.

12.2 Pharmacodynamics

Cardiac Electrophysiology

The effect of SPRAVATO (84 mg nasal spray and 0.8 mg/kg esketamine intravenously infused over 40 minutes) on the QTc interval was evaluated in a randomized, double-blind, placebo-, and positive-controlled (moxifloxacin 400 mg), 4-period, crossover study in 60 healthy subjects. A large increase in heart rate (i.e., >10 bpm) was observed in both intranasal and intravenous esketamine treatment groups. The totality of evidence from the nonclinical and clinical data indicates a lack of clinically relevant QTc prolongation at the therapeutic dose of esketamine.

12.3 Pharmacokinetics

Esketamine exposure increases with dose from 28 mg to 84 mg. The increase in Cmaxand AUC values was less than dose-proportional between 28 mg and 56 mg or 84 mg, but it was nearly dose proportional between 56 mg and 84 mg. No accumulation of esketamine in plasma was observed following twice a week administration.

Absorption

The mean absolute bioavailability is approximately 48% following nasal spray administration.

The time to reach maximum esketamine plasma concentration is 20 to 40 minutes after the last nasal spray of a treatment session.

The inter-subject variability of esketamine ranges from 27% to 66% for Cmaxand 18% to 45% for AUC∞. The intra-subject variability of esketamine is approximately 15% for Cmaxand 10% for AUC∞.

Distribution

The mean steady-state volume of distribution of esketamine administered by the intravenous route is 709 L.

Protein binding of esketamine was approximately 43% to 45%.

The brain-to-plasma ratio of noresketamine is 4- to 6-times lower than that of esketamine.

Elimination

After Cmaxwas reached following intranasal administration, the decline in plasma esketamine concentrations was biphasic, with rapid decline for the initial 2 to 4 hours and a mean terminal half-life (t1/2) that ranged from 7 to 12 hours. The mean clearance of esketamine is approximately 89 L/hour following intravenous administration. The elimination of the major metabolite, noresketamine, from plasma is slower than esketamine. The decline of noresketamine plasma concentrations is biphasic, with rapid decline for the initial 4 hours and a mean terminal t1/2of approximately 8 hours.

Metabolism

Esketamine is primarily metabolized to noresketamine metabolite via cytochrome P450 (CYP) enzymes CYP2B6 and CYP3A4 and to a lesser extent CYP2C9 and CYP2C19. Noresketamine is metabolized via CYP-dependent pathways and certain subsequent metabolites undergo glucuronidation.

Excretion

Less than 1% of a dose of nasal esketamine is excreted as unchanged drug in urine. Following intravenous or oral administration, esketamine-derived metabolites were primarily recovered in urine (≥ 78% of a radiolabeled dose) and to a lesser extent in feces (≤ 2% of a radiolabeled dose).

Specific Populations

Exposures of esketamine in specific populations are summarized in Figure 1. No significant differences in the pharmacokinetics of SPRAVATO nasal spray were observed for sex and total body weight (>39 to 170 kg) based on population PK analysis. There is no clinical experience with SPRAVATO nasal spray in patients on renal dialysis or with severe (Child-Pugh class C) hepatic impairment.

Figure 1: Effect of Specific Populations on the Pharmacokinetics of Esketamine

Drug Interaction Studies

The effect of other drugs on the exposures of intranasally administered esketamine are summarized in Figure 2. The effect of SPRAVATO on the exposures of other drugs are summarized in Figure 3. Based on these results, none of the drug-drug interactions are clinically significant.

Figure 2: Effect of Co-administered Drugs on the Pharmacokinetics of Esketamine

Figure 3: Effect of Esketamine on the Pharmacokinetics of Co-Administered Drugs

In Vitro Studies

Enzyme Systems: Esketamine has modest induction effects on CYP2B6 and CYP3A4 in human hepatocytes. Esketamine and its major metabolites do not induce CYP1A2. Esketamine and its major circulating metabolites did not show inhibition potential against CYPs and UGTs, except for a weak reversible inhibition of noresketamine on CYP3A4.

Transporter Systems: Esketamine is not a substrate of transporters P-glycoprotein (P-gp; multidrug resistance protein 1), breast cancer resistance protein (BCRP), or organic anion transporter (OATP) 1B1, or OATP1B3. Esketamine and its major circulating metabolites do not inhibit these transporters or multi-drug and toxin extrusion 1 (MATE1) and MATE2-K, or organic cation transporter 2 (OCT2), OAT1, or OAT3.

13 NONCLINICAL TOXICOLOGY

13.1 Carcinogenesis, Mutagenesis, Impairment of Fertility

Carcinogenesis

Once-daily intranasal administration of esketamine at doses equivalent to 4.5, 15, and 45 mg/kg/day (based on a 200-gram rat) did not increase the incidence of tumors in a 2-year rat carcinogenicity study. At the highest dose, the AUC exposure to esketamine was lower than the human exposure (AUC) at the maximum recommended human dose (MRHD) of 84 mg. Once-daily subcutaneous administration of esketamine up to 75 mg/kg/day (reduced to 40 mg/kg/day during week 17) did not increase the incidence of tumors in a 6-month study in transgenic (Tg.rasH2) mice.

Mutagenesis

Esketamine was not mutagenic with or without metabolic activation in the Ames test. Genotoxic effects with esketamine were seen in a screening in vitromicronucleus test in the presence of metabolic activation. However, intravenously-administered esketamine was devoid of genotoxic properties in an in vivobone marrow micronucleus test in rats and an in vivoComet assay in rat liver cells.

Impairment of Fertility

Esketamine was administered intranasally to both male and female rats before mating, throughout the mating period, and up to day 7 of gestation at doses equivalent to 4.5, 15, and 45 mg/kg/day (based on a 200-gram rat), which are approximately 0.05, 0.3, and 0.6-times the maximum recommended human dose (MRHD) of 84 mg/day based on mean AUC exposures, respectively. Estrous cycle irregularities were observed at the high dose of 45 mg/kg/day and increased time to mate was observed at doses ≥ 15 mg/kg/day without an overall effect on mating or fertility indices. The No Observed Adverse Effect Level (NOAEL) for mating and fertility is 45 mg/kg/day which is 0.6 times the esketamine exposures at MRHD of 84 mg/day.

13.2 Animal Toxicology and/or Pharmacology

Neurotoxicity

In a single-dose neuronal toxicity study where esketamine was administered intranasally to adult female rats, there were no findings of neuronal vacuolation in the brain up to an estimated dose equivalent of 45 mg/kg for a 200-gram rat with a safety margin of 1.8 and 4.5 times the clinical exposures for AUC and Cmax, respectively, to the MRHD of 84 mg/day. In a second single-dose neurotoxicity study conducted with intranasally administered esketamine to adult female rats, there were no findings of neuronal necrosis up to a dose equivalent of 270 mg/kg for a 200-gram rat which has a safety margin of 18-fold and 23-fold, respectively, to AUC and Cmaxexposures at the MRHD of 84 mg/day. Neuronal vacuolation was not examined in this study.

In a single-dose neuronal toxicity study in adult rats, subcutaneously administered racemic ketamine caused neuronal vacuolation in layer I of the retrosplenial cortex of the brain without neuronal necrosis at a dose of 60 mg/kg. The NOAEL for vacuolation in this study was 15 mg/kg. Estimating 50% of the exposure to be from esketamine, the NOAEL for neuronal vacuolation is 1.6-times and 4.5-times and the NOAEL for neuronal necrosis is 10-times and 16-times exposures, respectively, for AUC and Cmaxto the clinical exposure at the MRHD of 84 mg/day. The relevance of these findings to humans is unknown.

14 CLINICAL STUDIES

14.1 Treatment-Resistant Depression

Short-Term Study

SPRAVATO was evaluated in a randomized, placebo-controlled, double-blind, multicenter, short-term (4-week), Phase 3 study (Study 1; NCT02418585) in adult patients 18 to <65 years old with treatment-resistant depression (TRD). Patients in Study 1 met DSM-5 criteria for major depressive disorder (MDD) and in the current depressive episode, had not responded adequately to at least two different antidepressants of adequate dose and duration. After discontinuing prior antidepressant treatments, patients in Study 1 were randomized to receive twice weekly doses of intranasal SPRAVATO (flexible dose; 56 mg or 84 mg) or intranasal placebo. All patients also received open-label concomitant treatment with a newly initiated daily oral antidepressant (AD) (duloxetine, escitalopram, sertraline, or extended-release venlafaxine as determined by the investigator based on patient's prior treatment history). SPRAVATO could be titrated up to 84 mg starting with the second dose based on investigator discretion.

The demographic and baseline disease characteristics of patients in Study 1 were similar for the SPRAVATO and placebo nasal spray groups. Patients had a median age of 47 years (range 19 to 64 years) and were 62% female, 93% Caucasian, and 5% Black. The newly initiated oral AD was an SSRI in 32% of patients and an SNRI in 68% of patients.

In Study 1, the primary efficacy measure was change from baseline in the Montgomery-Åsberg Depression Rating Scale (MADRS) total score at the end of the 4-week double-blind induction phase. The MADRS is a ten-item, clinician-rated scale used to assess severity of depressive symptoms. Scores on the MADRS range from 0 to 60, with higher scores indicating more severe depression. SPRAVATO plus a newly initiated oral AD demonstrated statistical superiority on the primary efficacy measure compared to placebo nasal spray plus a newly initiated oral AD (see Table 10).

Table 10: Primary Efficacy Results for Change from Baseline in MADRS Total Score at Week 4 in Patients with TRD in Study 1
Treatment Group | Number of Patients | Mean Baseline Score (SD) | LS Mean (SE) Change from Baseline to end of Week 4 | LS Mean Difference (95% CI) [Difference (SPRAVATO + Oral AD minus Placebo nasal spray + Oral AD) in least-squares mean change from baseline]
SPRAVATO (56 mg or 84 mg) + Oral AD [SPRAVATO + Oral AD was statistically significantly superior to placebo nasal spray + oral AD] | 114 | 37.0 (5.7) | -19.8 (1.3) | -4.0 (-7.3; -0.6)
Placebo nasal spray + Oral AD | 109 | 37.3 (5.7) | -15.8 (1.3) | -
SD=standard deviation; SE=standard error; LS Mean=least-squares mean; CI=confidence interval; AD=antidepressant

Time Course of Treatment Response

Figure 4 shows the time course of response for the primary efficacy measure (MADRS) in Study 1. Most of SPRAVATO's treatment difference compared to placebo was observed at 24 hours. Between 24 hours and Day 28, both the SPRAVATO and placebo groups continued to improve; the difference between the groups generally remained but did not appear to increase over time through Day 28. At Day 28, 67% of the patients randomized to SPRAVATO were receiving 84 mg twice weekly.

Figure 4: Least Squares Mean Change from Baseline in MADRS Total Score Over Time in Patients with TRD in Study 1 [Note: In this flexible-dose study, dosing was individualized based on efficacy and tolerability. Few subjects (<10%) had reduction in SPRAVATO dosage from 84 mg to 56 mg twice weekly.] (Full Analysis Set)

Treatment-Resistant Depression – Long-term Study

Study 2 (NCT02493868) was a long-term randomized, double-blind, parallel-group, multicenter maintenance-of-effect study in adults 18 to <65 years of age who were known remitters and responders to SPRAVATO. Patients in this study were responders in one of two short-term controlled trials (Study 1 and another 4-week study) or in an open-label direct-enrollment study in which they received flexibly-dosed SPRAVATO (56 mg or 84 mg twice weekly) plus daily oral AD in an initial 4-week phase.

Stable remission was defined as a MADRS total score ≤ 12 for at least 3 of the last 4 weeks. Stable response was defined as a MADRS total score reduction ≥ 50% for the last 2 weeks of optimization and not in remission. After at least 16 initial weeks of treatment with SPRAVATO and an oral AD, stable remitters and stable responders were randomized separately to continue intranasal treatment with SPRAVATO or switch to placebo nasal spray, in both cases with continuation of their oral AD. The primary study endpoint was time to relapse in the stable remitter group. Relapse was defined as a MADRS total score ≥22 for 2 consecutive weeks or hospitalization for worsening depression or any other clinically relevant event indicative of relapse.

The demographic and baseline disease characteristics of the two groups were similar. Patients had a median age of 48 years (range 19 to 64 years) and were 66% female, 90% Caucasian, and 4% Black.

Patients in stable remission who continued treatment with SPRAVATO plus oral AD experienced a statistically significantly longer time to relapse of depressive symptoms than did patients on placebo nasal spray plus an oral AD (see Figure 5).

Figure 5: Time to Relapse in Patients with TRD in Stable Remission in Study 2 [Note: The estimated hazard ratio (95% CI) of SPRAVATO + Oral AD relative to Placebo nasal spray + Oral AD based on weighted estimates was 0.49 (95% CI: 0.29, 0.84). However, the hazard ratio did not appear constant throughout the trial.] (Full Analysis Set)

Time to relapse was also significantly delayed in the stable responder population. These patients experienced a statistically significantly longer time to relapse of depressive symptoms than patients on placebo nasal spray plus oral AD (see Figure 6).

Figure 6: Time to Relapse in Patients in Stable Response in Patients with TRD in Study 2 [Note: The estimated hazard ratio (95% CI) of SPRAVATO + Oral AD relative to Placebo nasal spray + Oral AD based on Cox proportional hazards model was 0.30 (95% CI: 0.16, 0.55).] (Full Analysis Set)

In Study 2, based on depressive symptomatology, the majority of stable remitters (69%) received every-other-week dosing for the majority of time during the maintenance phase; 23% of stable remitters received weekly dosing. Among stable responders, 34% received every-other-week dosing and 55% received weekly dosing the majority of time during the maintenance phase. Of the patients randomized to SPRAVATO, 39% received the 56 mg dose and 61% received the 84 mg dose.

Monotherapy Study

SPRAVATO was evaluated in a randomized, double-blind, placebo-controlled, multicenter study (Study 3; NCT04599855) in adult patients with treatment resistant depression (TRD) to evaluate the efficacy, safety, and tolerability of SPRAVATO nasal spray, 56 mg and 84 mg, administered as monotherapy. Patients in Study 3 met DSM-5 criteria for major depressive disorder (MDD) and in the current depressive episode, had not responded adequately to at least two different antidepressants of adequate dose and duration. After discontinuing prior antidepressant treatments if applicable, patients in Study 3 were randomized in a 1:1:2 ratio to receive twice weekly doses of intranasal SPRAVATO 56 mg or 84 mg or intranasal placebo for four weeks.

The demographic and baseline disease characteristics of patients in Study 3 were similar for the SPRAVATO and placebo nasal spray groups. Patients had a median age of 46 years (range 19 to 76 years) and were 61% female, 87% Caucasian, and 7% Black.

In Study 3, the primary efficacy measure was change from baseline in the (MADRS) total score at Day 28. SPRAVATO 56 mg and 84 mg monotherapy demonstrated statistical superiority on the primary efficacy measure compared to placebo nasal spray (see Table 11).

Table 11: Primary Efficacy Results for Change from Baseline in MADRS Total Score at Day 28 in Patients with TRD in Study 3
Treatment Group | Number of Patients | Mean Baseline Score (SD) | LS Mean (SE) Change from Baseline at Day 28 | LS Mean Difference (95% CI) [Difference (SPRAVATO minus Placebo nasal spray) in least-squares mean change from baseline]
SPRAVATO (56 mg) [SPRAVATO monotherapy is statistically significantly superior to placebo nasal spray] | 86 | 37.5 (5.2) | -11.4 (1.2) | -5.1 (-7.9; -2.3)
SPRAVATO (84 mg) | 95 | 36.6 (4.5) | -13.0 (1.2) | -6.8 (-9.5; -4.1)
Placebo nasal spray | 197 | 37.5 (4.9) | -6.3 (0.8) | -
SD=standard deviation; SE=standard error; LS Mean=least-squares mean; CI=confidence interval

In Study 3 the key secondary endpoint was change from baseline to Day 2 (approximately 24 hours) in the MADRS total score. The improvement at Day 2 by SPRAVATO 56 mg and 84 mg monotherapy demonstrated statistical superiority when compared to placebo nasal spray.

Time Course of Treatment Response

Figure 7 shows the time course of response for the primary efficacy measure (MADRS) in Study 3. The effect of SPRAVATO (56 mg and 84 mg) was observed at Day 2 (approximately 24 hours) and remained through Day 28.

Figure 7: Least Squares Mean Change from Baseline in MADRS Total Score Over Time in Patients with TRD in Study 3 (Full Analysis Set)

14.2 Depressive Symptoms in Patients with Major Depressive Disorder with Acute Suicidal Ideation or Behavior

SPRAVATO was evaluated in two identical Phase 3 short-term (4-week) randomized, double-blind, multicenter, placebo-controlled studies, Study 4 (NCT03039192) and Study 5 (NCT03097133), in adults with moderate-to-severe MDD (MADRS total score >28) who had active suicidal ideation and intent. In these studies, patients received treatment with SPRAVATO 84 mg or placebo nasal spray twice-weekly for 4 weeks. After the first dose, a one-time dose reduction to SPRAVATO 56 mg was allowed for patients unable to tolerate the 84 mg dose. All patients received comprehensive standard of care treatment, including an initial inpatient psychiatric hospitalization and a newly initiated or optimized oral antidepressant (AD) (AD monotherapy or AD plus augmentation therapy) as determined by the investigator. After completion of the 4-week treatment period with SPRAVATO/placebo, study follow-up continued through Day 90.

The baseline demographic and disease characteristics of patients in Study 4 and Study 5 were similar between the SPRAVATO plus standard of care or placebo nasal spray plus standard of care treatment groups. The median patient age was 40 years (range 18 to 64 years), 61% were female; 73% Caucasian and 6% Black; and 63% of patients had at least one prior suicide attempt. Prior to entering the study, 92% of the patients were receiving antidepressant therapy. During the study, as part of standard of care treatment, 40% of patients received AD monotherapy, 54% of patients received AD plus augmentation therapy, and 6% received both AD monotherapy/AD plus augmentation therapy.

The primary efficacy measure was the change from baseline in the MADRS total score at 24 hours after first dose (Day 2). In Study 4 and Study 5, SPRAVATO plus standard of care demonstrated statistical superiority on the primary efficacy measure compared to placebo nasal spray plus standard of care (see Table 12).

Table 12: Primary Efficacy Results for Change from Baseline in MADRS Total Score at 24 Hours After First Dose (Studies 4 and 5)
Study No. | Treatment Group [SOC treatment included an initial inpatient psychiatric hospitalization and a newly initiated or optimized oral antidepressant (antidepressant monotherapy or antidepressant monotherapy plus augmentation therapy).] | Number of Patients | Mean Baseline Score (SD) | LS Mean Change from Baseline to 24 hr Post First Dose (SE) | LS Mean Difference (95% CI) [Difference (SPRAVATO + SOC minus placebo nasal spray + SOC) in least-squares mean change from baseline.]
Study 4 | SPRAVATO 84 mg + SOC [SPRAVATO + SOC were statistically significantly superior to placebo nasal spray + SOC.] | 111 | 41.3 (5.87) | -15.9 (1.04) | -3.8 (-6.56; -1.09)
Study 4 | Placebo nasal spray + SOC | 112 | 41.0 (6.29) | -12.0 (1.02) | -
Study 5 | SPRAVATO 84 mg + SOC | 113 | 39.4 (5.21) | -16.0 (1.02) | -3.9 (-6.60; -1.11)
Study 5 | Placebo nasal spray + SOC | 113 | 39.9 (5.76) | -12.2 (1.05) | -
SD=standard deviation; SE=standard error; LS Mean=least-squares mean; CI=confidence interval; SOC=standard of care.

The secondary efficacy measure was the change in Clinical Global Impression of Suicidal Severity - Revised (CGI-SS-r) score at 24 hours after first dose (Day 2). The CGI-SS-r is a one-item, clinician-rated assessment used to rate the current severity of a patient's suicidal ideation and behavior. Scores on the CGI-SS-r range from 0 to 6, with higher scores indicating more severe suicidal ideation and behavior. In Study 4 and Study 5, SPRAVATO plus standard of care did not demonstrate superiority compared to placebo nasal spray plus standard of care in improving CGI-SS-r.

Time Course of Treatment Response

In both Study 4 and Study 5, SPRAVATO's treatment difference compared to placebo was observed starting at 4 hours. Between 4 hours and Day 25, both the SPRAVATO and placebo groups continued to improve; the difference between the groups generally remained but did not appear to increase over time through Day 25. Figure 8 depicts time course of the primary efficacy measure of change in MADRS total score from Study 4.

Figure 8: Least Squares Mean Change from Baseline in MADRS Total Score Over Time in Study 4 [Note: In Study 4, after the first dose, a one-time dose reduction to SPRAVATO 56 mg was allowed for patients unable to tolerate the 84 mg dose. Approximately 19% of patients had reduction in SPRAVATO dosage from 84 mg to 56 mg twice weekly.] (Full Analysis Set)

14.3 Special Safety Studies

Effects on Driving

Two studies were conducted to assess the effects of SPRAVATO on driving skills; one study in adult patients with major depressive disorder (Study 6) and one study in healthy subjects (Study 7). On-road driving performance was assessed by the mean standard deviation of the lateral position (SDLP), a measure of driving impairment.

A single-blind, placebo-controlled study in 25 adult patients with major depressive disorder evaluated the effects of a single 84 mg dose of intranasal SPRAVATO on next day driving and the effect of repeated administration of 84 mg of intranasal SPRAVATO on same-day driving performance (Study 6). For the single dose treatment phase, an ethanol-containing beverage was used as a positive control. The SDLP after administration of single 84 mg dose of SPRAVATO nasal spray was similar to placebo 18 hours post-dose. For the multiple dose treatment phase, the SDLP after repeated administration of 84 mg intranasal SPRAVATO was similar to placebo 6 hours post-dose on Day 11, Day 18, and Day 25.

A randomized, double-blind, cross-over, placebo-controlled study in 23 healthy subjects evaluated the effects of a single 84-mg dose of esketamine nasal spray on driving (Study 7). Mirtazapine (30 mg) was used as a positive control. Driving performance was assessed at 8 hours after SPRAVATO or mirtazapine administration. The SDLP 8 hours after SPRAVATO nasal spray administration was similar to placebo. Two subjects discontinued the driving test after receiving SPRAVATO because of a perceived inability to drive after experiencing post-dose adverse reactions; one subject reported pressure behind the eyes and paresthesia of the hands and feet, the other reported headache with light sensitivity and anxiety.

16 HOW SUPPLIED/STORAGE AND HANDLING

SPRAVATO®nasal spray is available as an aqueous solution of esketamine hydrochloride in a stoppered glass vial within a nasal spray device. Each nasal spray device delivers two sprays containing a total of 28 mg of esketamine (supplied as 32.3 mg of esketamine hydrochloride).

SPRAVATO is available in the following presentations:

- 56 mg Dose Kit: Unit-dose carton containing two 28 mg nasal spray devices (56 mg total dose) (NDC 50458-028-02).
- 84 mg Dose Kit: Unit-dose carton containing three 28 mg nasal spray devices (84 mg total dose) (NDC 50458-028-03).

Within each kit, each 28 mg device is individually packaged in a sealed blister (NDC 50458-028-00).

Storage

Store at 20° to 25°C (68° to 77°F); excursions permitted from 15° to 30°C (59° to 86°F) [see USP Controlled Room Temperature].

Disposal

SPRAVATO nasal spray devices must be handled with adequate security, accountability, and proper disposal, per facility procedure for a Schedule III drug product, and per applicable federal, state, and local regulations.

17 PATIENT COUNSELING INFORMATION

Advise the patient to read the FDA-approved patient labeling (Medication Guide).

Sedation, Dissociation, and Respiratory Depression

Inform patients that SPRAVATO has potential to cause sedation, dissociative symptoms (including perception disturbances), dizziness, vertigo, anxiety, and respiratory depression. Advise patients that they will need to be observed by a healthcare provider until these effects resolve [see Boxed Warning, Warnings and Precautions (5.1, 5.2, 5.3)] .

Potential for Abuse, Misuse, and Dependence

Advise patients that SPRAVATO is a federally controlled substance because it can be abused or lead to dependence [see Warnings and Precautions (5.4), Drug Abuse and Dependence (9)].

SPRAVATO Risk Evaluation and Mitigation Strategy (REMS)

SPRAVATO is available only through a restricted program called the SPRAVATO REMS [see Warnings and Precautions (5.5)] . Inform the patient of the following notable requirements:

- Patients treated in outpatient healthcare settings (e.g. medical offices and clinics) must be enrolled in the SPRAVATO REMS Program prior to administration.
- SPRAVATO must be administered under the direct observation of a healthcare provider.
- Patients must be monitored by a healthcare provider for at least 2 hours after administration of SPRAVATO .

Suicidal Thoughts and Behaviors

Advise patients and caregivers to look for the emergence of suicidality, especially early during treatment and when the dosage is adjusted [see Boxed Warningand Warnings and Precautions (5.6)] .

Increases in Blood Pressure

Advise patients that SPRAVATO can cause increases in blood pressure. Inform patients that after treatment sessions they should be advised that they may need to be observed by a healthcare provider until these effects resolve [see Warnings and Precautions (5.7)] .

Impaired Ability to Drive and Operate Machinery

Caution patients that SPRAVATO may impair their ability to drive or operate machinery. Instruct patients not to engage in potentially hazardous activities requiring complete mental alertness and motor coordination such as driving a motor vehicle or operating machinery until the next day after a restful sleep. Advise patients that they will need someone to drive them home after each treatment session [see Warnings and Precautions (5.9)] .

Pregnancy

Advise pregnant women and women of reproductive potential of the potential risk to a fetus. Advise patients to notify their healthcare provider if they are pregnant or intend to become pregnant during treatment with SPRAVATO. Advise patients that there is a pregnancy exposure registry that monitors pregnancy outcomes in women exposed to SPRAVATO during pregnancy [see Use in Specific Populations (8.1)] .

Lactation

Advise women not to breastfeed during treatment with SPRAVATO [see Use in Specific Populations (8.2)] .

Manufactured for:
Janssen Pharmaceuticals, Inc.
Titusville, NJ 08560, USA

For patent information: www.janssenpatents.com
© 2019 Janssen Pharmaceutical Companies

MEDICATION GUIDE
SPRAVATO®(sprah vah toe)
(esketamine)
nasal spray, CIII

What is the most important information I should know about SPRAVATO?

SPRAVATO can cause serious side effects, including:

- Sedation, dissociation, and respiratory depression. SPRAVATO may cause sleepiness (sedation), fainting, dizziness, spinning sensation, anxiety, or feeling disconnected from yourself, your thoughts, feelings, space and time (dissociation), and breathing problems (respiratory depression and respiratory arrest).
  - Tell your healthcare provider right away if you feel like you cannot stay awake or if you feel like you are going to pass out.
  - Your healthcare provider must monitor you for serious side effects for at least 2 hours after taking SPRAVATO. Your healthcare provider will decide when you are ready to leave the healthcare setting.
- Abuse and misuse.There is a risk for abuse and misuse with SPRAVATO, which may lead to physical and psychological dependence. Your healthcare provider should check you for signs of abuse, misuse, and dependence before and during treatment.
  - Tell your healthcare provider if you have ever abused or been dependent on alcohol, prescription medicines, or street drugs.
  - Your healthcare provider can tell you more about the differences between physical and psychological dependence in drug addiction.
- SPRAVATO Risk Evaluation and Mitigation Strategy (REMS).Because of the risks for sedation, dissociation, respiratory depression, abuse and misuse, SPRAVATO is only available through a restricted program called the SPRAVATO Risk Evaluation and Mitigation Strategy (REMS) Program. SPRAVATO can only be administered at healthcare settings certified in the SPRAVATO REMS Program. Patients treated in outpatient healthcare settings (such as medical offices and clinics) must be enrolled in the program.
- Increased risk of suicidal thoughts and actions.Antidepressant medicines may increase suicidal thoughts and actions in some people 24 years of age and younger, especially within the first few months of treatment or when the dose is changed. SPRAVATO is not for use in children.
  - Depression and other serious mental illnesses are the most important causes of suicidal thoughts and actions. Some people may have a higher risk of having suicidal thoughts and actions. These include people who have (or have a family history of) depression or a history of suicidal thoughts and actions.
  How can I watch for and try to prevent suicidal thoughts and actions in myself or a family member?
  - Pay close attention to any changes, especially sudden changes, in mood, behavior, thoughts, or feelings, or if you develop suicidal thoughts or actions.
  - Tell your healthcare provider right away if you have any new or sudden changes in mood, behavior, thoughts, or feelings, or if you develop suicidal thoughts or actions.
  - Keep all follow-up visits with your healthcare provider as scheduled. Call your healthcare provider between visits as needed, especially if you have concerns about symptoms.
  Tell your healthcare provider or get emergency help right away if you or your family member have any of the following symptoms, especially if they are new, worse, or worry you:

- thoughts about suicide or dying
- new or worse depression
- feeling very agitated or restless
- trouble sleeping (insomnia)
- acting aggressive, being angry, or violent
- an extreme increase in activity and talking (mania)

- suicide attempts
- new or worse anxiety
- panic attacks
- new or worse irritability
- acting on dangerous impulses
- other unusual changes in behavior or mood

See “ What are the possible side effects of SPRAVATO?” for more information about side effects.

What is SPRAVATO?

SPRAVATO is a prescription medicine used:

- with or without an antidepressant taken by mouth, to treat adults with treatment-resistant depression (TRD).
- with an antidepressant taken by mouth, to treat depressive symptoms in adults with major depressive disorder (MDD) with suicidal thoughts or actions.

SPRAVATO is not for use as a medicine to prevent or relieve pain (anesthetic). It is not known if SPRAVATO is safe and effective as an anesthetic medicine.

It is not known if SPRAVATO is safe and effective for use in preventing suicide or in reducing suicidal thoughts or actions. SPRAVATO is not for use in place of hospitalization if your healthcare provider determines that hospitalization is needed, even if improvement is experienced after the first dose of SPRAVATO.

It is not known if SPRAVATO is safe and effective in children.

Do not take SPRAVATO if you:

- have blood vessel (aneurysmal vascular) disease (including in the brain, chest, abdominal aorta, arms and legs)
- have an abnormal connection between your veins and arteries (arteriovenous malformation)
- have a history of bleeding in the brain
- are allergic to esketamine, ketamine, or any of the other ingredients in SPRAVATO. See the end of this Medication Guide for a complete list of ingredients in SPRAVATO.

If you are not sure if you have any of the above conditions, talk to your healthcare provider before taking SPRAVATO.

Before you take SPRAVATO, tell your healthcare provider about all of your medical conditions, including if you:

- have heart or brain problems, including:
  - high blood pressure (hypertension)
  - slow or fast heartbeats that cause shortness of breath, chest pain, lightheadedness, or fainting
  - history of heart attack
  - history of stroke
  - heart valve disease or heart failure
  - history of brain injury or any condition where there is increased pressure in the brain
- have liver problems
- have ever had a condition called "psychosis" (see, feel, or hear things that are not there, or believe in things that are not true).
- are pregnant or plan to become pregnant. SPRAVATO may harm your unborn baby. You should not take SPRAVATO if you are pregnant.
  - Tell your healthcare provider right away if you become pregnant during treatment with SPRAVATO.
  - If you are able to become pregnant, talk to your healthcare provider about methods to prevent pregnancy during treatment with SPRAVATO.
  - There is a pregnancy registry for women who are exposed to SPRAVATO during pregnancy. The purpose of the registry is to collect information about the health of women exposed to SPRAVATO and their baby. If you become pregnant during treatment with SPRAVATO, talk to your healthcare provider about registering with the National Pregnancy Registry for Antidepressants at 1-844-405-6185 or online at https://womensmentalhealth.org/clinical-and-research-programs/pregnancyregistry/antidepressants/.
- are breastfeeding or plan to breastfeed. SPRAVATO passes into your breast milk. You should not breastfeed during treatment with SPRAVATO.

Tell your healthcare provider about all the medicines that you take,including prescription and over-the-counter medicines, vitamins and herbal supplements. Taking SPRAVATO with certain medicines may cause side effects.

Especially tell your healthcare provider if you takecentral nervous system (CNS) depressants, psychostimulants, or monoamine oxidase inhibitors (MAOIs) medicines. Ask your healthcare provider if you are not sure if you take these medicines. Your healthcare provider can tell you if it is safe to take SPRAVATO with your other medicines.
Know the medicines you take. Keep a list of them to show to your healthcare provider and pharmacist when you get a new medicine.

How will I take SPRAVATO?

- You will take SPRAVATO nasal spray yourself, under the supervision of a healthcare provider in a healthcare setting. Your healthcare provider will show you how to use the SPRAVATO nasal spray device.
- Your healthcare provider will tell you how much SPRAVATO you will take and when you will take it.
- Follow your SPRAVATO treatment schedule exactly as your healthcare provider tells you to.
- During and after each use of the SPRAVATO nasal spray device, you will be checked by a healthcare provider who will decide when you are ready to leave the healthcare setting.
- You will need to plan for a caregiver or family member to drive you home after taking SPRAVATO.
- If you miss a SPRAVATO treatment, your healthcare provider may change your dose and treatment schedule.
- Some people taking SPRAVATO get nausea and vomiting. You should not eat for at least 2 hours before taking SPRAVATO and not drink liquids at least 30 minutes before taking SPRAVATO.
- If you take a nasal corticosteroid or nasal decongestant medicine, take these medicines at least 1 hour before taking SPRAVATO.

What should I avoid while taking SPRAVATO?

- Do notdrive, operate machinery, or do anything where you need to be completely alert after taking SPRAVATO. Do nottake part in these activities until the next day following a restful sleep. See " What is the most important information I should know about SPRAVATO?"

What are the possible side effects of SPRAVATO?

SPRAVATO may cause serious side effects, including:

- See " What is the most important information I should know about SPRAVATO?"
- Increased blood pressure.SPRAVATO can cause a temporary increase in your blood pressure that may last for about 4 hours after taking a dose. Your healthcare provider will check your blood pressure before taking SPRAVATO and for at least 2 hours after you take SPRAVATO. Tell your healthcare provider right away if you get chest pain, shortness of breath, sudden severe headache, change in vision, or seizures after taking SPRAVATO.
- Problems with thinking clearly.Tell your healthcare provider if you have problems thinking or remembering.
- Bladder problems.Tell your healthcare provider if you develop trouble urinating, such as a frequent or urgent need to urinate, pain when urinating, or urinating frequently at night.

The most common side effects of SPRAVATO include:

- feeling disconnected from yourself, your thoughts, feelings and things around you
- dizziness
- nausea
- feeling sleepy
- spinning sensation
- decreased feeling of sensitivity (numbness)

- feeling anxious
- lack of energy
- increased blood pressure
- vomiting
- feeling drunk
- headache
- feeling very happy or excited

If these common side effects occur, they usually happen right after taking SPRAVATO and go away the same day.

These are not all the possible side effects of SPRAVATO.

Call your doctor for medical advice about side effects. You may report side effects to FDA at 1-800-FDA-1088.

General information about SPRAVATO.

Medicines are sometimes prescribed for purposes other than those listed in a Medication Guide. You can ask your pharmacist or healthcare provider for information about SPRAVATO that is written for healthcare providers.

What are the ingredients in SPRAVATO?

Active ingredient: esketamine hydrochloride
Inactive ingredients:citric acid monohydrate, edetate disodium, sodium hydroxide, and water for injection

Manufactured for: Janssen Pharmaceuticals, Inc., Titusville, NJ 08560, USA
For patent information: www.janssenpatents.com
© 2019 Janssen Pharmaceutical Companies
For more information, go to www.SPRAVATO.com or call 1-800-526-7736.

This Medication Guide has been approved by the U.S. Food and Drug Administration.

Revised: 01/2025

INSTRUCTIONS FOR USE

SPRAVATO®
(SPRAH VAH' TOE) CIII
(esketamine)
Nasal Spray Device

28 mg per device
Each device delivers two sprays containing a total of 28 mg of esketamine.

Important

This device is intended for administration by the patient, under supervision of a healthcare professional. Read this Instructions for Use in full before training and supervising patient.

Need help?

For additional assistance or to share your feedback call 800-JANSSEN (800-526-7736).

Before first device only:

Instruct patient to blow nose before first device only.

Confirm required number of devices.

Healthcare professional:

- Check expiration date ('EXP').
  If expired, get a new device.
- Peel blister and remove device.

Healthcare professional:

- Do not prime device.
  This will result in a loss of medication.
- Check that indicator shows 2 green dots. If not, dispose of device and get a new one.
- Hand device to patient.

Instruct the patient to:

- Hold device as shown with the thumb gently supporting the plunger.
- Do notpress the plunger.

Instruct the patient to:

- Recline head at about 45 degreesduring administration to keep medication inside the nose.

Instruct the patient to:

- Insert tip straight into the first nostril.
- Nose rest should touch the skin between the nostrils.

Instruct the patient to:

- Close opposite nostril.
- Breathe in through nosewhile pushing plunger all the way up until it stops.

Instruct the patient to:

- Sniff gentlyafter spraying to keep medication inside nose.

Instruct the patient to:

- Switch hands to insert tip into the second nostril.
- Repeat Step 4 to deliver second spray.

Healthcare professional:

- Take device from patient.
- Check that indicator shows no green dots.If you see a green dot, have patient spray again into the second nostril.
- Check indicator again to confirm device is empty.

Instruct the patient to:

- Rest in a comfortable position (preferably, semi-reclined) for 5 minutes after each device.
- If liquid drips out, dab nose with a tissue.

Do notblow nose.

Healthcare professional:

- Repeat Steps 2–5for the next device.

This Instructions for Use has been approved by the U.S. Food and Drug Administration.

Manufactured for:
Janssen Pharmaceuticals, Inc.
Titusville, NJ 08560

Revised: November 2019

© 2019 Janssen Pharmaceutical Companies

PRINCIPAL DISPLAY PANEL - Two 28 mg Device Blister Pack Kit

NDC 50458-028-02

Spravato™
(esketamine)
nasal spray

CIII

56 mg Dose Kit

Two 28 mg
Nasal Spray Devices

56 mg dose = 2 devices (4 sprays)

Each device delivers two sprays
containing a total of 28 mg
of esketamine.

Attention: Dispense the enclosed
Medication Guide to each patient.

FOR INTRANASAL USE ONLY

Rx only

Unit-Dose Container:
Two 28 mg devices (56 mg dose)

PRINCIPAL DISPLAY PANEL - Three 28 mg Device Blister Pack Kit

NDC 50458-028-03

Spravato™
(esketamine)
nasal spray

CIII

84 mg Dose Kit

Three 28 mg
Nasal Spray Devices

84 mg dose = 3 devices (6 sprays)

Each device delivers two sprays
containing a total of 28 mg
of esketamine.

Attention: Dispense the enclosed
Medication Guide to each patient.

FOR INTRANASAL USE ONLY

Rx only

Unit-Dose Container:
Three 28 mg devices (84 mg dose)